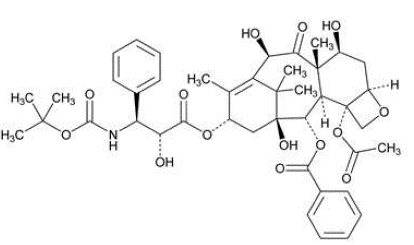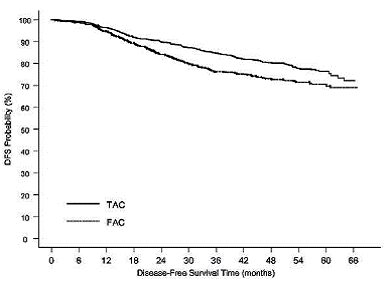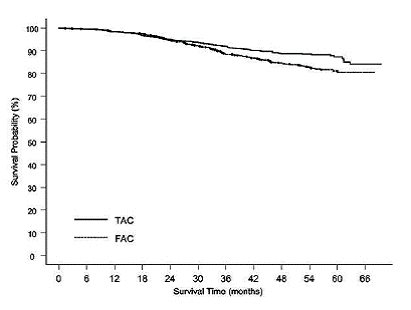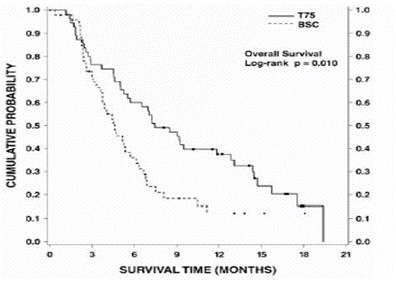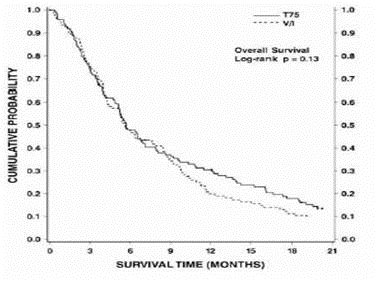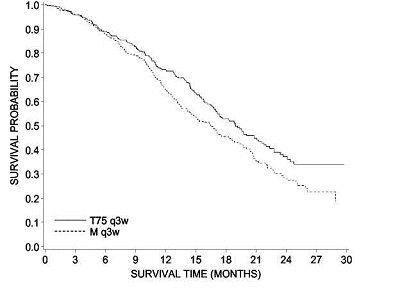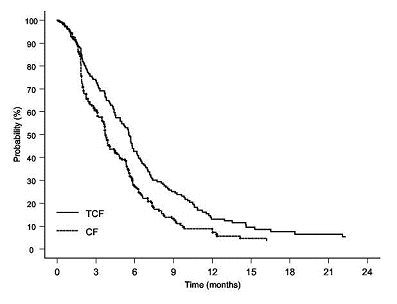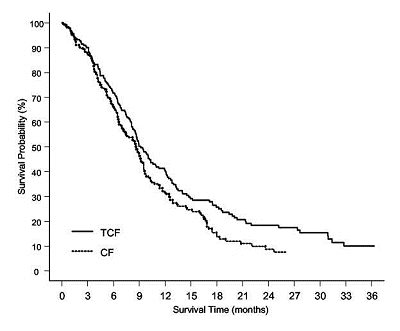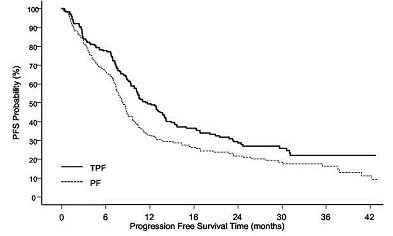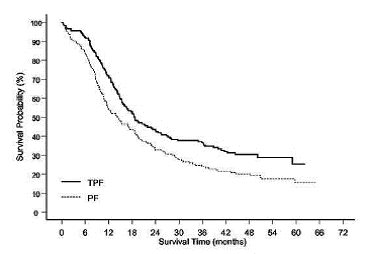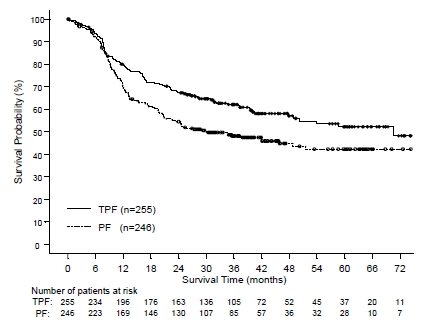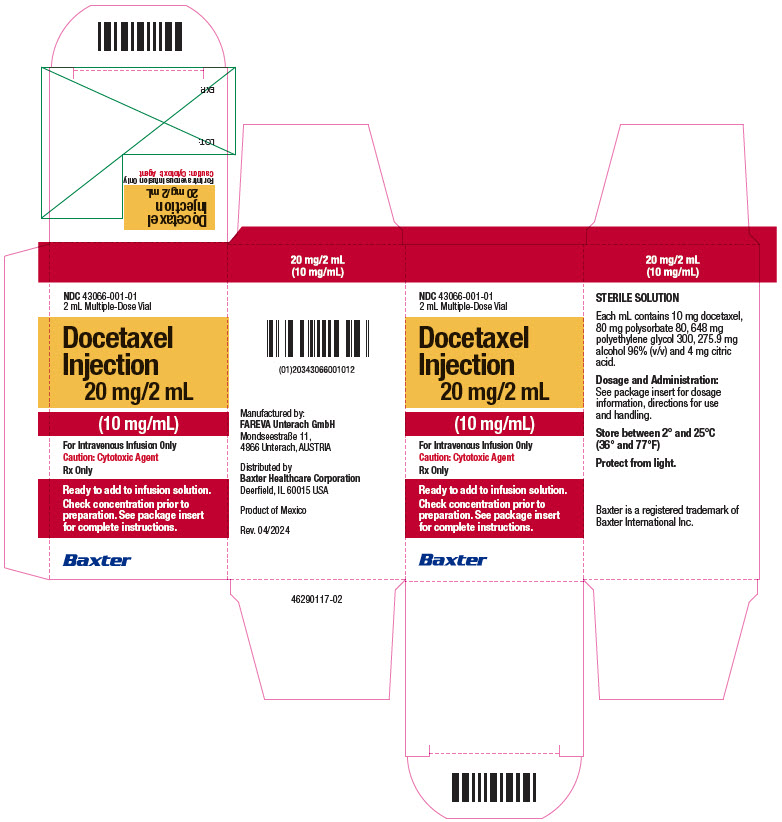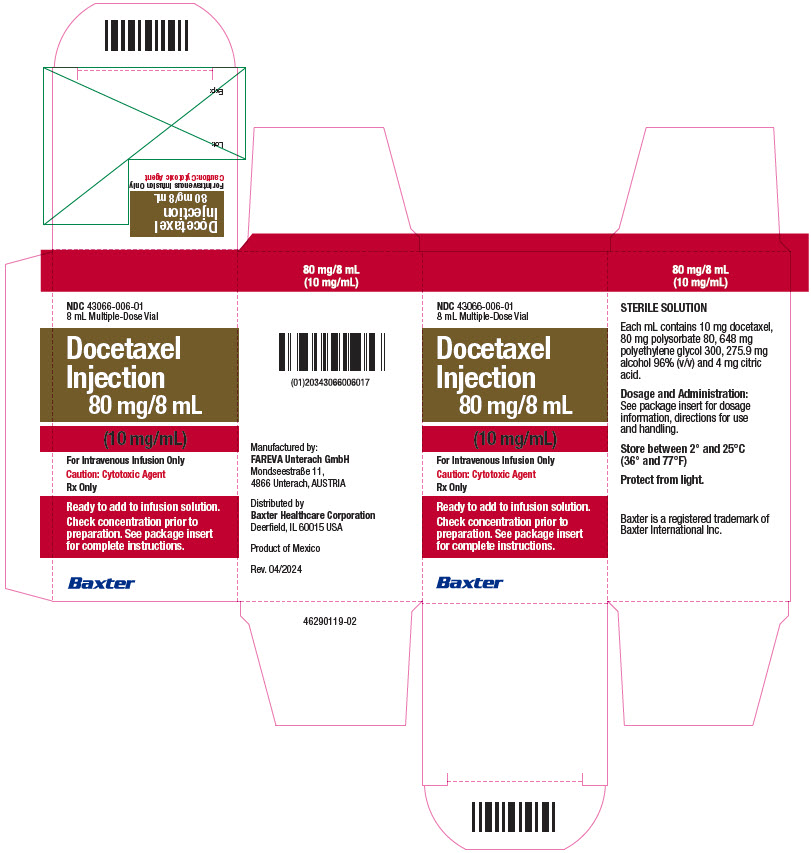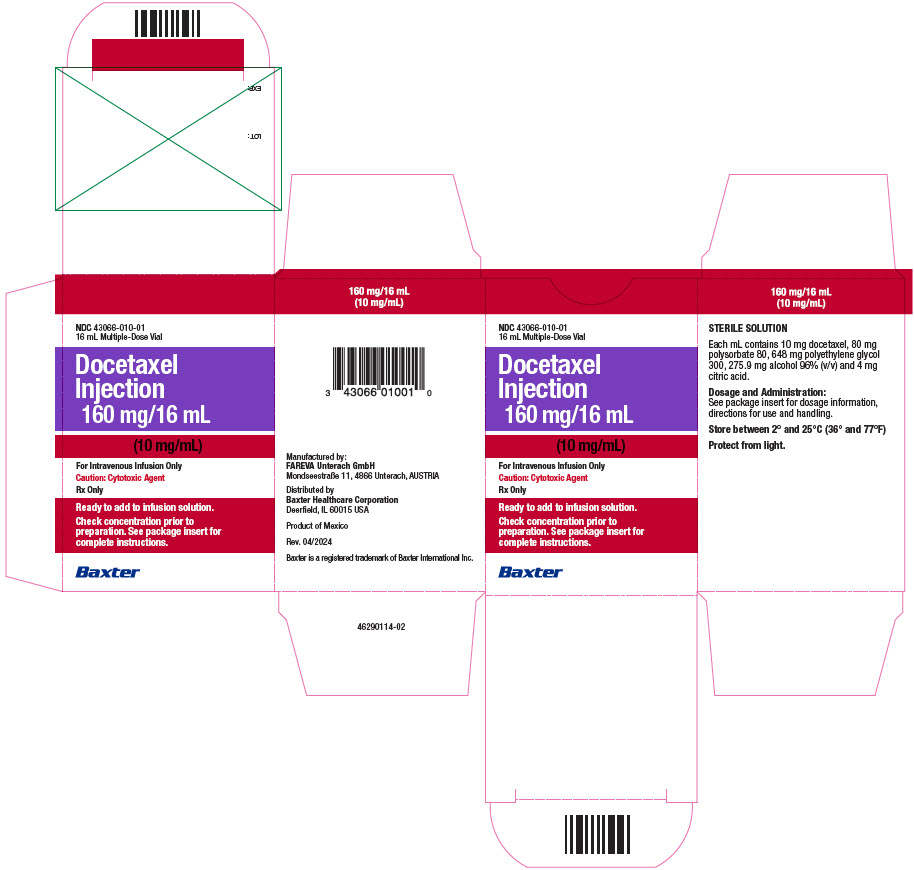 DRUG LABEL: Docetaxel
NDC: 43066-001 | Form: INJECTION, SOLUTION
Manufacturer: Baxter Healthcare Corporation
Category: prescription | Type: HUMAN PRESCRIPTION DRUG LABEL
Date: 20231121

ACTIVE INGREDIENTS: DOCETAXEL 10 mg/1 mL
INACTIVE INGREDIENTS: POLYSORBATE 80 80 mg/1 mL; ALCOHOL 275.9 mg/1 mL; POLYETHYLENE GLYCOL 300 648 mg/1 mL; CITRIC ACID MONOHYDRATE 4 mg/1 mL

HIGHLIGHTS OF PRESCRIBING INFORMATION

These highlights do not include all the information needed to use DOCETAXEL INJECTION safely and effectively. See full prescribing information for DOCETAXEL INJECTION.
DOCETAXEL INJECTION, for intravenous use
Initial U.S. Approval: 1996

WARNING: TOXIC DEATHS, HEPATOTOXICITY, NEUTROPENIA, HYPERSENSITIVITY REACTIONS, and FLUID RETENTION

See full prescribing information for complete boxed warning.

- Treatment-related mortality increases with abnormal liver function, at higher doses, and in patients with NSCLC and prior platinum-based therapy receiving docetaxel at 100 mg/m^2 (5.1)
- Avoid use of docetaxel if bilirubin > ULN, or if AST and/or ALT > 1.5 x ULN concomitant with alkaline phosphatase > 2.5 x ULN. LFT elevations increase risk of severe or life-threatening complications. Obtain LFTs before each treatment cycle (5.2)
- Do not administer docetaxel to patients with neutrophil counts < 1500 cells/ mm^3. Obtain frequent blood counts to monitor for neutropenia (4, 5.3)
- Severe hypersensitivity, including fatal anaphylaxis, has been reported in patients who received dexamethasone premedication. Severe reactions require immediate discontinuation of Docetaxel Injection and administration of appropriate therapy (5.5)
- Contraindicated if history of severe hypersensitivity reactions to docetaxel or to drugs formulated with polysorbate 80 (4)
- Severe fluid retention may occur despite dexamethasone (5.6)

1. INDICATIONS AND USAGE

Docetaxel Injection is a microtubule inhibitor indicated for:

- Breast Cancer (BC): single agent for locally advanced or metastatic BC after chemotherapy failure; and with doxorubicin and cyclophosphamide as adjuvant treatment of operable node-positive BC (1.1)
- Non-Small Cell Lung Cancer (NSCLC): single agent for locally advanced or metastatic NSCLC after platinum therapy failure; and with cisplatin for unresectable, locally advanced or metastatic untreated NSCLC (1.2)
- Castration-Resistant Prostate Cancer (CRPC): with prednisone in metastatic castration-resistant prostate cancer (1.3)
- Gastric Adenocarcinoma (GC): with cisplatin and fluorouracil for untreated, advanced GC, including the gastroesophageal junction (1.4)
- Squamous Cell Carcinoma of the Head and Neck (SCCHN): with cisplatin and fluorouracil for induction treatment of locally advanced SCCHN (1.5)

2. DOSAGE AND ADMINISTRATION

Administer in a facility equipped to manage possible complications (e.g., anaphylaxis). Administer intravenously (IV) over 1 hour every 3 weeks. PVC equipment is not recommended.

- BC locally advanced or metastatic: 60 mg/m^2 to 100 mg/m^2 single agent (2.1)
- BC adjuvant: 75 mg/m^2 administered 1 hour after doxorubicin 50 mg/m^2 and cyclophosphamide 500 mg/m^2 every 3 weeks for 6 cycles (2.1)
- NSCLC: after platinum therapy failure: 75 mg/m^2 single agent (2.2)
- NSCLC: chemotherapy-naive: 75 mg/m^2 followed by cisplatin 75 mg/m^2 (2.2)
- CRPC: 75 mg/m^2 with 5 mg prednisone twice a day continuously (2.3)
- GC: 75 mg/m^2 followed by cisplatin 75 mg/m^2 (both on day 1 only) followed by fluorouracil 750 mg/m^2 per day as a 24-hr IV (days 1-5), starting at end of cisplatin infusion (2.4)
- SCCHN: 75 mg/m^2 followed by cisplatin 75 mg/m^2 IV (day 1), followed by fluorouracil 750 mg/m^2 per day as a 24-hr IV (days 1-5), starting at end of cisplatin infusion; for 4 cycles (2.5)
- SCCHN: 75 mg/m^2 followed by cisplatin 100 mg/m^2 IV (day 1), followed by fluorouracil 1000 mg/m^2 per day as a 24-hr IV (days 1-4); for 3 cycles (2.5)

For all patients:

- Pre-medicate with oral corticosteroids (2.6)
- Adjust dose as needed (2.7)

3. DOSAGE FORMS AND STRENGTHS

- Multiple-dose vial 20 mg/2 mL, 80 mg/8 mL and 160 mg/16 mL (3)

4. CONTRAINDICATIONS

- Hypersensitivity to docetaxel or polysorbate 80 (4)
- Neutrophil counts of < 1500 cells/mm^3 (4)

5. WARNINGS AND PRECAUTIONS

- Second primary malignancies: In patients treated with docetaxel-containing regimens, monitor for delayed AML, MDS, NHL, and renal cancer. (5.7)
- Cutaneous reactions: Reactions including erythema of the extremities with edema followed by desquamation may occur. Severe cutaneous adverse reactions have been reported. Severe skin toxicity may require dose adjustment or permanent treatment discontinuation. (5.8)
- Neurologic reactions: Reactions including paresthesia, dysesthesia, and pain may occur. Severe neurosensory symptoms require dose adjustment or discontinuation if persistent. (5.9)
- Eye disorders: Cystoid macular edema (CME) has been reported and requires treatment discontinuation. (5.10)
- Asthenia: Severe asthenia may occur and may require treatment discontinuation. (5.11)
- Embryo-fetal toxicity: Can cause fetal harm. Advise patients of the potential risk to a fetus and to use effective contraception. (5.12, 8.1, 8.3)
- Alcohol content: The alcohol content in a dose of Docetaxel Injection may affect the central nervous system. This may include impairment of a patient’s ability to drive or use machines immediately after infusion. (5.13)
- Tumor lysis syndrome: Tumor lysis syndrome has been reported. Patients at risk should be well hydrated and closely monitored during treatment. (5.14)

6. ADVERSE REACTIONS

Most common adverse reactions across all docetaxel indications are infections, neutropenia, anemia, febrile neutropenia, hypersensitivity, thrombocytopenia, neuropathy, dysgeusia, dyspnea, constipation, anorexia, nail disorders, fluid retention, asthenia, pain, nausea, diarrhea, vomiting, mucositis, alopecia, skin reactions, and myalgia. (6)

To report SUSPECTED ADVERSE REACTIONS, contact Sandoz Inc., at 1-800-525-8747 or FDA at 1-800-FDA-1088 or www.fda.gov/medwatch.

7. DRUG INTERACTIONS

- Cytochrome P450 3A4 inducers, inhibitors, or substrates: May alter docetaxel metabolism. (7)

8. USE IN SPECIFIC POPULATIONS

- Lactation: Advise women not to breastfeed. (8.2)
- Females and Males of Reproductive Potential: Verify pregnancy status of females prior to initiation of Docetaxel Injection. (8.3)

FULL PRESCRIBING INFORMATION

WARNING: TOXIC DEATHS, HEPATOTOXICITY, NEUTROPENIA, HYPERSENSITIVITY REACTIONS, and FLUID RETENTION

Treatment-related mortality associated with docetaxel is increased in patients with abnormal liver function, in patients receiving higher doses, and in patients with non-small cell lung carcinoma and a history of prior treatment with platinum-based chemotherapy who receive docetaxel as a single agent at a dose of 100 mg/m^2 [see Warnings and Precautions (5.1)].

Avoid the use of Docetaxel Injection in patients with bilirubin > upper limit of normal (ULN), or to patients with AST and/or ALT >1.5 x ULN concomitant with alkaline phosphatase >2.5 x ULN. Patients with elevations of bilirubin or abnormalities of transaminase concurrent with alkaline phosphatase are at increased risk for the development of severe neutropenia, febrile neutropenia, infections, severe thrombocytopenia, severe stomatitis, severe skin toxicity, and toxic death. Patients with isolated elevations of transaminase >1.5 x ULN also had a higher rate of febrile neutropenia. Measure bilirubin, AST or ALT, and alkaline phosphatase prior to each cycle of Docetaxel Injection [see Warnings and Precautions (5.2)].

Do not administer Docetaxel Injection to patients with neutrophil counts of <1500 cells/mm^3. Monitor blood counts frequently as neutropenia may be severe and result in infection [see Warnings and Precautions (5.3)].

Do not administer Docetaxel Injection to patients who have a history of severe hypersensitivity reactions to Docetaxel Injection or to other drugs formulated with polysorbate 80 [see Contraindications (4)]. Severe hypersensitivity reactions have been reported in patients despite dexamethasone premedication. Hypersensitivity reactions require immediate discontinuation of the Docetaxel Injection infusion and administration of appropriate therapy [see Warnings and Precautions (5.5)].

Severe fluid retention occurred in 6.5% (6/92) of patients despite use of dexamethasone premedication. It was characterized by one or more of the following events: poorly tolerated peripheral edema, generalized edema, pleural effusion requiring urgent drainage, dyspnea at rest, cardiac tamponade, or pronounced abdominal distention (due to ascites) [see Warnings and Precautions (5.6)].

1. INDICATIONS AND USAGE

1.1 Breast Cancer

Docetaxel Injection is indicated for the treatment of patients with locally advanced or metastatic breast cancer after failure of prior chemotherapy.

Docetaxel Injection in combination with doxorubicin and cyclophosphamide is indicated for the adjuvant treatment of patients with operable node-positive breast cancer.

1.2 Non-Small Cell Lung Cancer

Docetaxel Injection as a single agent is indicated for the treatment of patients with locally advanced or metastatic non-small cell lung cancer after failure of prior platinum-based chemotherapy.

Docetaxel Injection in combination with cisplatin is indicated for the treatment of patients with unresectable, locally advanced or metastatic non-small cell lung cancer who have not previously received chemotherapy for this condition.

1.3 Prostate Cancer

Docetaxel Injection in combination with prednisone is indicated for the treatment of patients with metastatic castration-resistant prostate cancer.

1.4 Gastric Adenocarcinoma

Docetaxel Injection in combination with cisplatin and fluorouracil is indicated for the treatment of patients with advanced gastric adenocarcinoma, including adenocarcinoma of the gastroesophageal junction, who have not received prior chemotherapy for advanced disease.

1.5 Head and Neck Cancer

Docetaxel Injection in combination with cisplatin and fluorouracil is indicated for the induction treatment of patients with locally advanced squamous cell carcinoma of the head and neck (SCCHN).

2. DOSAGE AND ADMINISTRATION

For all indications, toxicities may warrant dosage adjustments [see Dosage and Administration (2.7)].

Administer in a facility equipped to manage possible complications (e.g., anaphylaxis).

2.1 Breast Cancer

- For locally advanced or metastatic breast cancer after failure of prior chemotherapy, the recommended dose of Docetaxel Injection is 60 mg/m^2 to 100 mg/m^2 administered intravenously over 1 hour every 3 weeks.
- For the adjuvant treatment of operable node-positive breast cancer, the recommended Docetaxel Injection dose is 75 mg/m^2 administered 1 hour after doxorubicin 50 mg/m^2 and cyclophosphamide 500 mg/m^2 every 3 weeks for 6 courses. Prophylactic G-CSF may be used to mitigate the risk of hematological toxicities [see Dosage and Administration (2.7)].

2.2 Non-Small Cell Lung Cancer

- For treatment after failure of prior platinum-based chemotherapy, docetaxel was evaluated as monotherapy, and the recommended dose is 75 mg/m^2 administered intravenously over 1 hour every 3 weeks. A dose of 100 mg/m^2 in patients previously treated with chemotherapy was associated with increased hematologic toxicity, infection, and treatment-related mortality in randomized, controlled trials [see Boxed Warning, Dosage and Administration (2.7), Warnings and Precautions (5), Clinical Studies (14)].
- For chemotherapy-naive patients, docetaxel was evaluated in combination with cisplatin. The recommended dose of Docetaxel Injection is 75 mg/m^2 administered intravenously over 1 hour immediately followed by cisplatin 75 mg/m^2 over 30-60 minutes every 3 weeks [see Dosage and Administration (2.7)].

2.3 Prostate Cancer

For metastatic castration-resistant prostate cancer, the recommended dose of Docetaxel Injection is 75 mg/m^2 every 3 weeks as a 1 hour intravenous infusion. Prednisone 5 mg orally twice daily is administered continuously [see Dosage and Administration (2.7)].

2.4 Gastric Adenocarcinoma

For gastric adenocarcinoma, the recommended dose of Docetaxel Injection is 75 mg/m^2 as a 1-hour intravenous infusion, followed by cisplatin 75 mg/m^2, as a 1- to 3- hour intravenous infusion (both on day 1 only), followed by fluorouracil 750 mg/m^2 per day given as a 24-hour continuous intravenous infusion for 5 days, starting at the end of the cisplatin infusion. Treatment is repeated every three weeks. Patients must receive premedication with antiemetics and appropriate hydration for cisplatin administration [see Dosage and Administration (2.7)].

2.5 Head and Neck Cancer

Patients must receive premedication with antiemetics, and appropriate hydration (prior to and after cisplatin administration). Prophylaxis for neutropenic infections should be administered. All patients treated on the docetaxel injection containing arms of the TAX323 and TAX324 studies received prophylactic antibiotics.

Induction Chemotherapy Followed by Radiotherapy (TAX323)

For the induction treatment of locally advanced inoperable SCCHN, the recommended dose of Docetaxel Injection is 75 mg/m^2 as a 1 -hour intravenous infusion followed by cisplatin 75 mg/m^2 intravenously over 1 hour, on day one, followed by fluorouracil as a continuous intravenous infusion at 750 mg/m^2 per day for five days. This regimen is administered every 3 weeks for 4 cycles. Following chemotherapy, patients should receive radiotherapy [see Dosage and Administration (2.7)].

Induction Chemotherapy Followed by Chemoradiotherapy (TAX324)

For the induction treatment of patients with locally advanced (unresectable, low surgical cure, or organ preservation) SCCHN, the recommended dose of Docetaxel Injection is 75 mg/m^2 as a 1-hour intravenous infusion on day 1, followed by cisplatin 100 mg/m^2 administered as a 30-minute to 3 hour infusion, followed by fluorouracil 1000 mg/m^2/day as a continuous infusion from day 1 to day 4. This regimen is administered every 3 weeks for 3 cycles. Following chemotherapy, patients should receive chemoradiotherapy [see Dosage and Administration (2.7)].

2.6 Premedication Regimen

All patients should be premedicated with oral corticosteroids (see below for prostate cancer) such as dexamethasone 16 mg per day (e.g., 8 mg twice daily) for 3 days starting 1 day prior to Docetaxel Injection administration in order to reduce the incidence and severity of fluid retention as well as the severity of hypersensitivity reactions [see Boxed Warning, Warnings and Precautions (5.5)].

For metastatic castration-resistant prostate cancer, given the concurrent use of prednisone, the recommended premedication regimen is oral dexamethasone 8 mg, at 12 hours, 3 hours and 1 hour before the Docetaxel Injection infusion [see Warnings and Precautions (5.5)].

2.7 Dosage Adjustments During Treatment

Breast Cancer

Patients who are dosed initially at 100 mg/m^2 and who experience either febrile neutropenia, neutrophils <500 cells/mm^3 for more than 1 week, or severe or cumulative cutaneous reactions during Docetaxel Injection therapy should have the dosage adjusted from 100 mg/m^2 to 75 mg/m^2. If the patient continues to experience these reactions, the dosage should either be decreased from 75 mg/m^2 to 55 mg/m^2 or the treatment should be discontinued. Conversely, patients who are dosed initially at 60 mg/m^2 and who do not experience febrile neutropenia, neutrophils <500 cells/mm^3 for more than 1 week, severe or cumulative cutaneous reactions, or severe peripheral neuropathy during Docetaxel Injection therapy may tolerate higher doses. Patients who develop ≥grade 3 peripheral neuropathy should have Docetaxel Injection treatment discontinued entirely.

Combination Therapy with Docetaxel Injection in the Adjuvant Treatment of Breast Cancer

Docetaxel Injection in combination with doxorubicin and cyclophosphamide should be administered when the neutrophil count is ≥1,500 cells/mm^3. Patients who experience febrile neutropenia should receive G-CSF in all subsequent cycles. Patients who continue to experience this reaction should remain on G-CSF and have their Docetaxel Injection dose reduced to 60 mg/m^2. Patients who experience grade 3 or 4 stomatitis should have their Docetaxel Injection dose decreased to 60 mg/m^2. Patients who experience severe or cumulative cutaneous reactions or moderate neurosensory signs and/or symptoms during Docetaxel Injection therapy should have their dosage of Docetaxel Injection reduced from 75 mg/m^2 to 60 mg/m^2. If the patient continues to experience these reactions at 60 mg/m^2, treatment should be discontinued.

Non-Small Cell Lung Cancer

Monotherapy with Docetaxel Injection for NSCLC treatment after failure of prior platinum-based chemotherapy

Patients who are dosed initially at 75 mg/m^2 and who experience either febrile neutropenia, neutrophils <500 cells/mm^3 for more than one week, severe or cumulative cutaneous reactions, or other grade 3/4 non-hematological toxicities during Docetaxel Injection treatment should have treatment withheld until resolution of the toxicity and then resumed at 55 mg/m^2. Patients who develop ≥grade 3 peripheral neuropathy should have Docetaxel Injection treatment discontinued entirely.

Combination therapy with Docetaxel Injection for chemotherapy-naive NSCLC

For patients who are dosed initially at Docetaxel Injection 75 mg/m^2 in combination with cisplatin, and whose nadir of platelet count during the previous course of therapy is <25,000 cells/mm^3, in patients who experience febrile neutropenia, and in patients with serious non-hematologic toxicities, the Docetaxel Injection dosage in subsequent cycles should be reduced to 65 mg/m^2. In patients who require a further dose reduction, a dose of 50 mg/m^2 is recommended. For cisplatin dosage adjustments, see manufacturers' prescribing information.

Prostate Cancer

Combination therapy with Docetaxel Injection for metastatic castration-resistant prostate cancer

Docetaxel Injection should be administered when the neutrophil count is ≥1,500 cells/mm^3. Patients who experience either febrile neutropenia, neutrophils <500 cells/mm^3 for more than one week, severe or cumulative cutaneous reactions or moderate neurosensory signs and/or symptoms during Docetaxel Injection therapy should have the dosage of Docetaxel Injection reduced from 75 mg/m^2 to 60 mg/m^2. If the patient continues to experience these reactions at 60 mg/m^2, the treatment should be discontinued.

Gastric or Head and Neck Cancer

Docetaxel Injection in combination with cisplatin and fluorouracil in gastric cancer or head and neck cancer

Patients treated with Docetaxel Injection in combination with cisplatin and fluorouracil must receive antiemetics and appropriate hydration according to current institutional guidelines. In both studies, G-CSF was recommended during the second and/or subsequent cycles in case of febrile neutropenia, or documented infection with neutropenia, or neutropenia lasting more than 7 days. If an episode of febrile neutropenia, prolonged neutropenia or neutropenic infection occurs despite G-CSF use, the Docetaxel Injection dose should be reduced from 75 mg/m^2 to 60 mg/m^2. If subsequent episodes of complicated neutropenia occur the Docetaxel Injection dose should be reduced from 60 mg/m^2 to 45 mg/m^2. In case of grade 4 thrombocytopenia the Docetaxel Injection dose should be reduced from 75 mg/m^2 to 60 mg/m^2. Do not retreat patients with subsequent cycles of Docetaxel Injection until neutrophils recover to a level >1,500 cells/mm^3 [see Contraindications (4)]. Avoid retreating patients until platelets recover to a level >100,000 cells/mm^3. Discontinue treatment if these toxicities persist [see Warnings and Precautions (5.3)].

Recommended dose modifications for toxicities in patients treated with Docetaxel Injection in combination with cisplatin and fluorouracil are shown in Table 1.

Table 1 - Recommended Dose Modifications for Toxicities in Patients Treated with Docetaxel Injection in Combination with Cisplatin and Fluorouracil

Toxicity | Dosage Adjustment
Diarrhea grade 3 | First episode: reduce fluorouracil dose by 20%.; Second episode: then reduce Docetaxel Injection dose by 20%.
Diarrhea grade 4 | First episode: reduce Docetaxel Injection and fluorouracil doses by 20%.; Second episode: discontinue treatment.
Stomatitis/mucositis grade 3 | First episode: reduce fluorouracil dose by 20%.; Second episode: stop fluorouracil only, at all subsequent cycles.; Third episode: reduce Docetaxel Injection dose by 20%.
Stomatitis/mucositis grade 4 | First episode: stop fluorouracil only, at all subsequent cycles.; Second episode: reduce Docetaxel Injection dose by 20%.

Liver dysfunction:

In case of AST/ALT >2.5 to ≤5 × ULN and AP ≤2.5 × ULN, or AST/ALT >1.5 to ≤5 × ULN and AP >2.5 to ≤5 × ULN, Docetaxel Injection should be reduced by 20%.

In case of AST/ALT >5 × ULN and/or AP >5 × ULN Docetaxel Injection should be stopped.

The dose modifications for cisplatin and fluorouracil in the gastric cancer study are provided below:

Cisplatin dose modifications and delays

Peripheral neuropathy: A neurological examination should be performed before entry into the study, and then at least every 2 cycles and at the end of treatment. In the case of neurological signs or symptoms, more frequent examinations should be performed and the following dose modifications can be made according to NCI-CTCAE grade:

- Grade 2: Reduce cisplatin dose by 20%.
- Grade 3: Discontinue treatment.

Ototoxicity: In the case of grade 3 toxicity, discontinue treatment.

Nephrotoxicity: In the event of a rise in serum creatinine ≥grade 2 (>1.5 × normal value) despite adequate rehydration, CrCl should be determined before each subsequent cycle and the following dose reductions should be considered (see Table 2).

For other cisplatin dosage adjustments, also refer to the manufacturers’ prescribing information.

Table 2 - Dose Reductions for Evaluation of Creatinine Clearance

Creatinine Clearance Result Before Next Cycle | Cisplatin Dose Next Cycle
CrCl ≥60 mL/min | Full dose of cisplatin was given. CrCl was to be repeated before each treatment cycle.
CrCl between 40 and 59 mL/min | Dose of cisplatin was reduced by 50% at subsequent cycle. If CrCl was >60 mL/min at end of cycle, full cisplatin dose was reinstituted at the next cycle.; If no recovery was observed, then cisplatin was omitted from the next treatment cycle.
CrCl <40 mL/min | Dose of cisplatin was omitted in that treatment cycle only.; If CrCl was still <40 mL/min at the end of cycle, cisplatin was discontinued.; If CrCl was >40 and <60 mL/min at end of cycle, a 50% cisplatin dose was given at the next cycle.; If CrCl was >60 mL/min at end of cycle, full cisplatin dose was given at next cycle.
CrCl = Creatinine clearance

Fluorouracil dose modifications and treatment delays

For diarrhea and stomatitis, see Table 1.

In the event of grade 2 or greater plantar-palmar toxicity, fluorouracil should be stopped until recovery. The fluorouracil dosage should be reduced by 20%.

For other greater than grade 3 toxicities, except alopecia and anemia, chemotherapy should be delayed (for a maximum of 2 weeks from the planned date of infusion) until resolution to grade ≤1 and then recommenced, if medically appropriate.

For other fluorouracil dosage adjustments, also refer to the manufacturers’ prescribing information.

Combination Therapy with Strong CYP3A4 Inhibitors:

Avoid using concomitant strong CYP3A4 inhibitors (e.g., ketoconazole, itraconazole, clarithromycin, atazanavir, indinavir, nefazodone, nelfinavir, ritonavir, saquinavir, telithromycin and voriconazole). There are no clinical data with a dose adjustment in patients receiving strong CYP3A4 inhibitors. Based on extrapolation from a pharmacokinetic study with ketoconazole in 7 patients, consider a 50% docetaxel dose reduction if patients require co-administration of a strong CYP3A4 inhibitor [see Drug Interactions (7), Clinical Pharmacology (12.3)].

2.8 Administration Precautions

Docetaxel Injection is a hazardous anticancer drug and, as with other potentially toxic compounds, caution should be exercised when handling and preparing Docetaxel Injection solutions. The use of gloves is recommended [see How Supplied/Storage and Handling (16.3)].

If Docetaxel Injection or diluted solution for intravenous infusion should come into contact with the skin, immediately and thoroughly wash with soap and water. If Docetaxel Injection or diluted solution for intravenous infusion should come into contact with mucosa, immediately and thoroughly wash with water.

Contact of the Docetaxel Injection with plasticized PVC equipment or devices used to prepare solutions for infusion is not recommended. In order to minimize patient exposure to the plasticizer DEHP (di-2-ethylhexyl phthalate), which may be leached from PVC infusion bags or sets, the Docetaxel Injection diluted solution for infusion should be stored in bottles (glass, polypropylene) or plastic bags (polypropylene, polyolefin) and administered through polyethylene-lined administration sets.

Docetaxel Injection requires NO prior dilution with a diluent and is ready to add to the infusion solution. Please follow the preparation instructions provided below.

2.9 Preparation and Administration

Dilution for Infusion

Using only a 21 gauge needle, aseptically withdraw the required amount of Docetaxel Injection solution (10 mg docetaxel/mL) with a calibrated syringe and inject (as a single injection) into a 250 mL infusion bag or bottle of either 0.9% Sodium Chloride solution or 5% Dextrose solution to produce a final concentration of 0.3 mg/mL to 0.74 mg/mL.

If a dose greater than 200 mg of Docetaxel Injection is required, use a larger volume of the infusion vehicle so that a concentration of 0.74 mg/mL Docetaxel Injection is not exceeded.

Thoroughly mix the infusion bag or bottle manually by gentle inversion and rotation in a controlled manner and avoid foaming. Shaking or vigorous agitation should be avoided during preparation and transportation to the patient for administration.

As with all parenteral products, Docetaxel Injection should be inspected visually for particulate matter or discoloration prior to administration whenever the solution and container permit. If the Docetaxel Injection vial or diluted solution is not clear or appears to have precipitation, these should be discarded.

The Docetaxel Injection diluted solution for infusion should be administered intravenously as a 1-hour infusion under ambient room temperature below 25ºC (77ºF) and lighting conditions.

2.10 Stability

Docetaxel Injection infusion solution, if stored between 2°C and 25°C (36°F and 77°F) is stable for 4 hours in either 0.9% Sodium Chloride solution or 5% Dextrose solution. Use within 4 hours including storage and administration. Do not freeze infusion solution.

3. DOSAGE FORMS AND STRENGTHS

- 20 mg/2 mL multiple-dose vial
- 80 mg/8 mL multiple-dose vial
- 160 mg/16 mL multiple-dose vial

4. CONTRAINDICATIONS

Docetaxel Injection is contraindicated in patients with:

- neutrophil counts of <1500 cells/mm^3 [see Warnings and Precautions (5.3)].
- a history of severe hypersensitivity reactions to docetaxel or to other drugs formulated with polysorbate 80. Severe reactions, including anaphylaxis, have occurred [see Warnings and Precautions (5.5)].

5. WARNINGS AND PRECAUTIONS

5.1 Toxic Deaths

Breast Cancer

Docetaxel administered at 100 mg/m^2 was associated with deaths considered possibly or probably related to treatment in 2.0% (19/965) of metastatic breast cancer patients, both previously treated and untreated, with normal baseline liver function and in 11.5% (7/61) of patients with various tumor types who had abnormal baseline liver function (AST and/or ALT >1.5 times ULN together with AP >2.5 times ULN). Among patients dosed at 60 mg/m^2, mortality related to treatment occurred in 0.6% (3/481) of patients with normal liver function, and in 3 of 7 patients with abnormal liver function. Approximately half of these deaths occurred during the first cycle. Sepsis accounted for the majority of the deaths.

Non-Small Cell Lung Cancer

Docetaxel administered at a dose of 100 mg/m^2 in patients with locally advanced or metastatic non-small cell lung cancer who had a history of prior platinum-based chemotherapy was associated with increased treatment-related mortality (14% and 5% in two randomized, controlled studies). There were 2.8% treatment-related deaths among the 176 patients treated at the 75 mg/m^2 dose in the randomized trials. Among patients who experienced treatment-related mortality at the 75 mg/m^2 dose level, 3 of 5 patients had an ECOG PS of 2 at study entry [see Dosage and Administration (2.2), Clinical Studies (14)].

5.2 Hepatic Impairment

Patients with elevations of bilirubin or abnormalities of transaminase concurrent with alkaline phosphatase are at increased risk for the development of severe neutropenia, febrile neutropenia, infections, severe thrombocytopenia, severe stomatitis, severe skin toxicity, and toxic death.

Avoid docetaxel in patients with bilirubin > upper limit of normal (ULN), or to patients with AST and/or ALT >1.5 x ULN concomitant with alkaline phosphatase >2.5 x ULN [see Warnings and Precautions (5.1)].

For patients with isolated elevations of transaminase >1.5 x ULN, consider docetaxel dose modifications [see Dosage and Administration (2.7)].

Measure bilirubin, AST or ALT, and alkaline phosphatase prior to each cycle of docetaxel therapy.

5.3 Hematologic Effects

Perform frequent peripheral blood cell counts on all patients receiving Docetaxel Injection. Do not retreat patients with subsequent cycles of Docetaxel Injection until neutrophils recover to a level >1500 cells/mm^3 [see Contraindications (4)]. Avoid retreating patients until platelets recover to a level > 100,000 cells/mm^3.

A 25% reduction in the dose of Docetaxel Injection is recommended during subsequent cycles following severe neutropenia (<500 cells/mm^3) lasting 7 days or more, febrile neutropenia, or a grade 4 infection in a Docetaxel Injection cycle [see Dosage and Administration (2.7)].

Neutropenia (<2000 neutrophils/mm^3) occurs in virtually all patients given 60 mg/m^2 to 100 mg/m^2 of docetaxel and grade 4 neutropenia (<500 cells/mm^3) occurs in 85% of patients given 100 mg/m^2 and 75% of patients given 60 mg/m^2. Frequent monitoring of blood counts is, therefore, essential so that dose can be adjusted. Docetaxel Injection should not be administered to patients with neutrophils <1500 cells/mm^3.

Febrile neutropenia occurred in about 12% of patients given 100 mg/m^2 but was very uncommon in patients given 60 mg/m^2. Hematologic responses, febrile reactions and infections, and rates of septic death for different regimens are dose related [see Adverse Reactions (6.1), Clinical Studies (14)].

Three breast cancer patients with severe liver impairment (bilirubin >1.7 times ULN) developed fatal gastrointestinal bleeding associated with severe drug-induced thrombocytopenia. In gastric cancer patients treated with docetaxel in combination with cisplatin and fluorouracil (TCF), febrile neutropenia and/or neutropenic infection occurred in 12% of patients receiving G-CSF compared to 28% who did not. Patients receiving TCF should be closely monitored during the first and subsequent cycles for febrile neutropenia and neutropenic infection [see Dosage and Administration (2.7), Adverse Reactions (6)].

5.4 Enterocolitis and Neutropenic Colitis

Enterocolitis and neutropenic colitis (typhlitis) have occurred in patients treated with docetaxel alone and in combination with other chemotherapeutic agents, despite the coadministration of G-CSF. Caution is recommended for patients with neutropenia, particularly at risk for developing gastrointestinal complications. Enterocolitis and neutropenic enterocolitis may develop at any time, and could lead to death as early as the first day of symptom onset. Monitor patients closely from onset of any symptoms of gastrointestinal toxicity. Inform patients to contact their healthcare provider with new, or worsening symptoms of gastrointestinal toxicity [see Dosage and Administration (2), Warnings and Precautions (5.3), Adverse Reactions (6.2)].

5.5 Hypersensitivity Reactions

Monitor patients closely for hypersensitivity reactions, especially during the first and second infusions. Severe hypersensitivity reactions characterized by generalized rash/erythema, hypotension and/or bronchospasm, or fatal anaphylaxis, have been reported in patients premedicated with 3 days of corticosteroids. Severe hypersensitivity reactions require immediate discontinuation of the Docetaxel Injection infusion and aggressive therapy. Do not rechallenge patients with a history of severe hypersensitivity reactions with Docetaxel Injection [see Contraindications (4)].

Patients who have previously experienced a hypersensitivity reaction to paclitaxel may develop a hypersensitivity reaction to docetaxel that may include severe or fatal reactions such as anaphylaxis. Monitor patients with a previous history of hypersensitivity to paclitaxel closely during initiation of docetaxel therapy.

Hypersensitivity reactions may occur within a few minutes following initiation of a Docetaxel Injection infusion. If minor reactions such as flushing or localized skin reactions occur, interruption of therapy is not required. All patients should be premedicated with an oral corticosteroid prior to the initiation of the infusion of Docetaxel Injection [see Dosage and Administration (2.6)].

5.6 Fluid Retention

Severe fluid retention has been reported following docetaxel therapy. Patients should be premedicated with oral corticosteroids prior to each Docetaxel Injection administration to reduce the incidence and severity of fluid retention [see Dosage and Administration (2.6)]. Patients with pre-existing effusions should be closely monitored from the first dose for the possible exacerbation of the effusions.

When fluid retention occurs, peripheral edema usually starts in the lower extremities and may become generalized with a median weight gain of 2 kg.

Among 92 breast cancer patients premedicated with 3-day corticosteroids, moderate fluid retention occurred in 27.2% and severe fluid retention in 6.5%. The median cumulative dose to onset of moderate or severe fluid retention was 819 mg/m^2. Nine of 92 patients (9.8%) of patients discontinued treatment due to fluid retention: 4 patients discontinued with severe fluid retention; the remaining 5 had mild or moderate fluid retention. The median cumulative dose to treatment discontinuation due to fluid retention was 1021 mg/m^2.

Fluid retention was completely, but sometimes slowly, reversible with a median of 16 weeks from the last infusion of docetaxel to resolution (range: 0 to 42+ weeks). Patients developing peripheral edema may be treated with standard measures, e.g., salt restriction, oral diuretic(s).

5.7 Second Primary Malignancies

Second primary malignancies, notably acute myeloid leukemia (AML), myelodysplastic syndrome (MDS), non-Hodgkin’s lymphoma (NHL), and renal cancer, have been reported in patients treated with docetaxel-containing regimens. These adverse reactions may occur several months or years after docetaxel-containing therapy.

Treatment-related AML or MDS has occurred in patients given anthracyclines and/or cyclophosphamide, including use in adjuvant therapy for breast cancer. In the adjuvant breast cancer trial (TAX316) AML occurred in 3 of 744 patients who received docetaxel, doxorubicin and cyclophosphamide (TAC) and in 1 of 736 patients who received fluorouracil, doxorubicin and cyclophosphamide [see Clinical Studies (14.2)]. In TAC-treated patients, the risk of delayed myelodysplasia or myeloid leukemia requires hematological follow-up. Monitor patients for second primary malignancies [see Adverse Reactions (6.1)].

5.8 Cutaneous Reactions

Localized erythema of the extremities with edema followed by desquamation has been observed. In case of severe skin toxicity, an adjustment in dosage is recommended [see Dosage and Administration (2.7)]. The discontinuation rate due to skin toxicity was 1.6% (15/965) for metastatic breast cancer patients. Among 92 breast cancer patients premedicated with 3-day corticosteroids, there were no cases of severe skin toxicity reported and no patient discontinued docetaxel due to skin toxicity.

Severe cutaneous adverse reactions (SCARs) such as Stevens-Johnson syndrome (SJS), toxic epidermal necrolysis (TEN), and acute generalized exanthematous pustulosis (AGEP) have been reported in association with docetaxel treatment. Patients should be informed about the signs and symptoms of serious skin manifestations and monitored closely. Permanent treatment discontinuation should be considered in patients who experience SCARs.

5.9 Neurologic Reactions

Severe neurosensory symptoms (e.g., paresthesia, dysesthesia, pain) were observed in 5.5% (53/965) of metastatic breast cancer patients and resulted in treatment discontinuation in 6.1%. When these symptoms occur, dosage must be adjusted. If symptoms persist, treatment should be discontinued [see Dosage and Administration (2.7)]. Patients who experienced neurotoxicity in clinical trials and for whom follow-up information on the complete resolution of the event was available had spontaneous reversal of symptoms with a median of 9 weeks from onset (range: 0 to 106 weeks). Severe peripheral motor neuropathy mainly manifested as distal extremity weakness occurred in 4.4% (42/965).

5.10 Eye Disorders

Cystoid macular edema (CME) has been reported in patients treated with docetaxel. Patients with impaired vision should undergo a prompt and comprehensive ophthalmologic examination. If CME is diagnosed, docetaxel treatment should be discontinued and appropriate treatment initiated. Alternative non-taxane cancer treatment should be considered.

5.11 Asthenia

Severe asthenia has been reported in 14.9% (144/965) of metastatic breast cancer patients but has led to treatment discontinuation in only 1.8%. Symptoms of fatigue and weakness may last a few days up to several weeks and may be associated with deterioration of performance status in patients with progressive disease.

5.12 Embryo-Fetal Toxicity

Based on findings from animal reproduction studies and its mechanism of action, docetaxel can cause fetal harm when administered to a pregnant woman [see Clinical Pharmacology (12.1)]. Available data from case reports in the literature and pharmacovigilance with docetaxel use in pregnant women are not sufficient to inform the drug-associated risk of major birth defects, miscarriage or adverse maternal or fetal outcomes. In animal reproduction studies, administration of docetaxel to pregnant rats and rabbits during the period of organogenesis caused embryo-fetal toxicities, including intrauterine mortality, at doses as low as 0.02 and 0.003 times the recommended human dose based on body surface area, respectively.

Advise pregnant women and females of reproductive potential of the potential risk to a fetus. Verify pregnancy status in females of reproductive potential prior to initiating docetaxel. Advise females of reproductive potential to use effective contraception during treatment and for 2 months after the last dose of Docetaxel Injection. Advise male patients with female partners of reproductive potential to use effective contraception during treatment and for 4 months after the last dose of Docetaxel Injection [see Use in Specific Populations (8.1, 8.3)].

5.13 Alcohol Content

Cases of intoxication have been reported with some formulations of docetaxel due to the alcohol content. The alcohol content in a dose of Docetaxel Injection may affect the central nervous system and should be taken into account for patients in whom alcohol intake should be avoided or minimized.

Consideration should be given to the alcohol content in Docetaxel Injection on the ability to drive or use machines immediately after the infusion. Each administration of Docetaxel Injection at 100 mg/m2 delivers 2.65 g/m2 of ethanol. For a patient with a BSA of 2.0 m2, this would deliver 5.3 grams of ethanol [see Description (11)]. Other docetaxel products may have a different amount of alcohol.

5.14 Tumor Lysis Syndrome

Tumor lysis syndrome has been reported with docetaxel [see Adverse Reactions (6.2)]. Patients at risk of tumor lysis syndrome (e.g., with renal impairment, hyperuricemia, bulky tumor) should be closely monitored prior to initiating Docetaxel Injection and periodically during treatment. Correction of dehydration and treatment of high uric acid levels are recommended prior to initiation of treatment.

6. ADVERSE REACTIONS

The most serious adverse reactions from docetaxel are:

- Toxic Deaths [see Boxed Warning, Warnings and Precautions (5.1)]
- Hepatic Impairment [see Boxed Warning, Warnings and Precautions (5.2)]
- Hematologic Effects [see Boxed Warning, Warnings and Precautions (5.3)]
- Enterocolitis and Neutropenic Colitis [see Warnings and Precautions (5.4)]
- Hypersensitivity Reactions [see Boxed Warning, Warnings and Precautions (5.5)]
- Fluid Retention [see Boxed Warning, Warnings and Precautions (5.6)]
- Second Primary Malignancies [see Warnings and Precautions (5.7)]
- Cutaneous Reactions [see Warnings and Precautions (5.8)]
- Neurologic Reactions [see Warnings and Precautions (5.9)]
- Eye Disorders [see Warnings and Precautions (5.10)]
- Asthenia [see Warnings and Precautions (5.11)]
- Alcohol Content [see Warnings and Precautions (5.13)]

The most common adverse reactions across all docetaxel indications are infections, neutropenia, anemia, febrile neutropenia, hypersensitivity, thrombocytopenia, neuropathy, dysgeusia, dyspnea, constipation, anorexia, nail disorders, fluid retention, asthenia, pain, nausea, diarrhea, vomiting, mucositis, alopecia, skin reactions, and myalgia. Incidence varies depending on the indication. Adverse reactions are described according to indication. Because clinical trials are conducted under widely varying conditions, adverse reaction rates observed in the clinical trials of a drug cannot be directly compared to rates in the clinical trials of another drug and may not reflect the rates observed in practice.

Responding patients may not experience an improvement in performance status on therapy and may experience worsening. The relationship between changes in performance status, response to therapy, and treatment-related side effects has not been established.

6.1 Clinical Trials Experience

Breast Cancer

Monotherapy with docetaxel for locally advanced or metastatic breast cancer after failure of prior chemotherapy

Docetaxel 100 mg/m^2: Adverse drug reactions occurring in at least 5% of patients are compared for three populations who received docetaxel administered at 100 mg/m^2 as a 1-hour infusion every 3 weeks: 2045 patients with various tumor types and normal baseline liver function tests; the subset of 965 patients with locally advanced or metastatic breast cancer, both previously treated and untreated with chemotherapy, who had normal baseline liver function tests; and an additional 61 patients with various tumor types who had abnormal liver function tests at baseline. These reactions were described using COSTART terms and were considered possibly or probably related to docetaxel. At least 95% of these patients did not receive hematopoietic support. The safety profile is generally similar in patients receiving docetaxel for the treatment of breast cancer and in patients with other tumor types (see Table 3).

Table 3 - Summary of Adverse Reactions in Patients Receiving Docetaxel at 100 mg/m^2

 | All Tumor Types | All Tumor Types | Breast Cancer
 | Normal LFTs [Normal Baseline LFTs: Transaminases ≤1.5 times ULN or alkaline phosphatase ≤2.5 times ULN or isolated elevations of transaminases or alkaline phosphatase up to 5 times ULN.] | Elevated LFTs [Elevated Baseline LFTs: AST and/or ALT >1.5 times ULN concurrent with alkaline phosphatase >2.5 times ULN.] | Normal LFTs
Adverse Reaction | n=2045; % | n=61; % | n=965; %
Hematologic
Neutropenia
<2000 cells/mm^3 | 96 | 96 | 99
<500 cells/mm^3 | 75 | 88 | 86
Leukopenia
<4000 cells/mm^3 | 96 | 98 | 99
<1000 cells/mm^3 | 32 | 47 | 44
Thrombocytopenia
<100,000 cells/mm^3 | 8 | 25 | 9
Anemia
<11 g/dL | 90 | 92 | 94
<8 g/dL | 9 | 31 | 8
Febrile Neutropenia [Febrile Neutropenia: ANC grade 4 with fever >38°C with intravenous antibiotics and/or hospitalization.] | 11 | 26 | 12
Septic Death | 2 | 5 | 1
Non-Septic Death | 1 | 7 | 1
Infections
Any | 22 | 33 | 22
Severe | 6 | 16 | 6
Fever in Absence of
Infection
Any | 31 | 41 | 35
Severe | 2 | 8 | 2
Hypersensitivity Reactions
Regardless of Premedication
Any | 21 | 20 | 18
Severe | 4 | 10 | 3
With 3-day Premedication | n=92 | n=3 | n=92
Any | 15 | 33 | 15
Severe | 2 | 0 | 2
Fluid Retention; Regardless of Premedication
Any; Severe; With 3-day Premedication; Any; Severe | 47; 7; n=92; 64; 7 | 39; 8; n=3; 67; 33 | 60; 9; n=92; 64; 7
Neurosensory
Any; Severe | 49; 4 | 34; 0 | 58; 6
Cutaneous
Any; Severe | 48; 5 | 54; 10 | 47; 5
Nail Changes
Any; Severe | 31; 3 | 23; 5 | 41; 4
Gastrointestinal
Nausea; Vomiting; Diarrhea; Severe | 39; 22; 39; 5 | 38; 23; 33; 5 | 42; 23; 43; 6
Stomatitis
Any; Severe | 42; 6 | 49; 13 | 52; 7
Alopecia | 76 | 62 | 74
Asthenia
Any; Severe | 62; 13 | 53; 25 | 66; 15
Myalgia
Any; Severe | 19; 2 | 16; 2 | 21; 2
Arthralgia | 9 | 7 | 8
Infusion Site Reactions | 4 | 3 | 4

Hematologic Reactions

Reversible marrow suppression was the major dose-limiting toxicity of docetaxel [see Warnings and Precautions (5.3)]. The median time to nadir was 7 days, while the median duration of severe neutropenia (<500 cells/mm^3) was 7 days. Among 2045 patients with solid tumors and normal baseline LFTs, severe neutropenia occurred in 75.4% and lasted for more than 7 days in 2.9% of cycles.

Febrile neutropenia (<500 cells/mm^3 with fever >38°C with intravenous antibiotics and/or hospitalization) occurred in 11% of patients with solid tumors, in 12.3% of patients with metastatic breast cancer, and in 9.8% of 92 breast cancer patients premedicated with 3-day corticosteroids.

Severe infectious episodes occurred in 6.1% of patients with solid tumors, in 6.4% of patients with metastatic breast cancer, and in 5.4% of 92 breast cancer patients premedicated with 3-day corticosteroids.

Thrombocytopenia (<100,000 cells/mm^3) associated with fatal gastrointestinal hemorrhage has been reported.

Hypersensitivity Reactions

Severe hypersensitivity reactions have been reported [see Boxed Warning, Warnings and Precautions (5.5)]. Minor events, including flushing, rash with or without pruritus, chest tightness, back pain, dyspnea, drug fever, or chills, have been reported and resolved after discontinuing the infusion and instituting appropriate therapy.

Fluid Retention

Fluid retention can occur with the use of docetaxel[see Boxed Warning, Dosage and Administration (2.6), Warnings and Precautions (5.6)].

Cutaneous Reactions

Severe skin toxicity is discussed elsewhere in the label [see Warnings and Precautions (5.8)]. Reversible cutaneous reactions characterized by a rash including localized eruptions, mainly on the feet and/or hands, but also on the arms, face, or thorax, usually associated with pruritus, have been observed. Eruptions generally occurred within 1 week after docetaxel infusion, recovered before the next infusion, and were not disabling.

Severe nail disorders were characterized by hypo- or hyperpigmentation, and occasionally by onycholysis (in 0.8% of patients with solid tumors) and pain.

Neurologic Reactions

Neurologic reactions are discussed elsewhere in the label [see Warnings and Precautions (5.9)].

Gastrointestinal Reactions

Nausea, vomiting, and diarrhea were generally mild to moderate. Severe reactions occurred in 3% - 5% of patients with solid tumors and to a similar extent among metastatic breast cancer patients. The incidence of severe reactions was 1% or less for the 92 breast cancer patients premedicated with 3-day corticosteroids.

Severe stomatitis occurred in 5.5% of patients with solid tumors, in 7.4% of patients with metastatic breast cancer, and in 1.1% of the 92 breast cancer patients premedicated with 3-day corticosteroids.

Cardiovascular Reactions

Hypotension occurred in 2.8% of patients with solid tumors; 1.2% required treatment. Clinically meaningful events such as heart failure, sinus tachycardia, atrial flutter, dysrhythmia, unstable angina, pulmonary edema, and hypertension have occurred. Seven of 86 (8.1%) of metastatic breast cancer patients receiving docetaxel 100 mg/m^2 in a randomized trial and who had serial left ventricular ejection fractions assessed developed deterioration of LVEF by ≥10% associated with a drop below the institutional lower limit of normal.

Infusion Site Reactions

Infusion site reactions were generally mild and consisted of hyperpigmentation, inflammation, redness or dryness of the skin, phlebitis, extravasation, or swelling of the vein.

Hepatic Reactions

In patients with normal LFTs at baseline, bilirubin values greater than the ULN occurred in 8.9% of patients. Increases in AST or ALT >1.5 times the ULN, or alkaline phosphatase >2.5 times ULN, were observed in 18.9% and 7.3% of patients, respectively. While on docetaxel, increases in AST and/or ALT >1.5 times ULN concomitant with alkaline phosphatase >2.5 times ULN occurred in 4.3% of patients with normal LFTs at baseline. Whether these changes were related to the drug or underlying disease has not been established.

Hematologic and Other Toxicity: Relation to dose and baseline liver chemistry abnormalities

Hematologic and other toxicity is increased at higher doses and in patients with elevated baseline liver function tests (LFTs). In the following tables, adverse drug reactions are compared for three populations: 730 patients with normal LFTs given docetaxel at 100 mg/m^2 in the randomized and single arm studies of metastatic breast cancer after failure of previous chemotherapy; 18 patients in these studies who had abnormal baseline LFTs (defined as AST and/or ALT >1.5 times ULN concurrent with alkaline phosphatase >2.5 times ULN); and 174 patients in Japanese studies given docetaxel at 60 mg/m^2 who had normal LFTs (see Tables 4 and 5).

Table 4 - Hematologic Adverse Reactions in Breast Cancer Patients Previously Treated with Chemotherapy Treated at Docetaxel 100 mg/m^2 with Normal or Elevated Liver Function Tests or 60 mg/m^2 with Normal Liver Function Tests

Adverse Reaction | Docetaxel 100 mg/m^2 |  | Docetaxel 60 mg/m^2
 | Normal LFTs [Normal Baseline LFTs: Transaminases ≤1.5 times ULN or alkaline phosphatase ≤2.5 times ULN or isolated elevations of transaminases or alkaline phosphatase up to 5 times ULN.] n=730; % | Elevated LFTs [Elevated Baseline LFTs: AST and/or ALT >1.5 times ULN concurrent with alkaline phosphatase >2.5 times ULN.]; n=18; % | Normal LFTs n=174; %
Neutropenia
Any <2000 cells/mm^3 | 98 | 100 | 95
Grade 4 <500 cells/mm^3 | 84 | 94 | 75
Thrombocytopenia
Any <100,000 cells/mm^3 | 11 | 44 | 14
Grade 4 <20,000 cells/mm^3 | 1 | 17 | 1
Anemia <11 g/dL | 95 | 94 | 65
Infection [Incidence of infection requiring hospitalization and/or intravenous antibiotics was 8.5% (n=62) among the 730 patients with normal LFTs at baseline; 7 patients had concurrent grade 3 neutropenia, and 46 patients had grade 4 neutropenia.]
Any | 23 | 39 | 1
Grade 3 and 4 | 7 | 33 | 0
Febrile Neutropenia [Febrile Neutropenia: For 100 mg/m^2, ANC grade 4 and fever >38°C with intravenous antibiotics and/or hospitalization; for 60 mg/m^2, ANC grade 3/4 and fever >38.1°C.]
By Patient | 12 | 33 | 0
By Course | 2 | 9 | 0
Septic Death | 2 | 6 | 1
Non-Septic Death | 1 | 11 | 0

Table 5 - Non-Hematologic Adverse Reactions in Breast Cancer Patients Previously Treated with Chemotherapy Treated at Docetaxel 100 mg/m^2 with Normal or Elevated Liver Function Tests or 60 mg/m^2 with Normal Liver Function Tests

Adverse Reaction | Docetaxel 100 mg/m^2 |  | Docetaxel 60 mg/m^2
 | Normal LFTs [Normal Baseline LFTs: Transaminases ≤1.5 times ULN or alkaline phosphatase ≤2.5 times ULN or isolated elevations of transaminases or alkaline phosphatase up to 5 times ULN.] n=730; % | Elevated LFTs [Elevated Baseline Liver Function: AST and/or ALT >1.5 times ULN concurrent with alkaline phosphatase >2.5 times ULN.] n=18; % | Normal; LFTs; n=174; %
Acute Hypersensitivity Reaction Regardless of Premedication
Any | 13 | 6 | 1
Severe | 1 | 0 | 0
Fluid Retention [Fluid Retention includes (by COSTART): edema (peripheral, localized, generalized, lymphedema, pulmonary edema, and edema otherwise not specified) and effusion (pleural, pericardial, and ascites); no premedication given with the 60 mg/m^2 dose.]; Regardless of Premedication
Any | 56 | 61 | 13
Severe | 8 | 17 | 0
Neurosensory
Any | 57 | 50 | 20
Severe | 6 | 0 | 0
Myalgia | 23 | 33 | 3
Cutaneous
Any | 45 | 61 | 31
Severe | 5 | 17 | 0
Asthenia
Any | 65 | 44 | 66
Severe | 17 | 22 | 0
Diarrhea
Any | 42 | 28 | NA
Severe | 6 | 11
Stomatitis
Any | 53 | 67 | 19
Severe | 8 | 39 | 1
NA = not available

In the three-arm monotherapy trial, TAX313, which compared docetaxel 60 mg/m^2, 75 mg/m^2 and 100 mg/m^2 in advanced breast cancer, grade 3/4 or severe adverse reactions occurred in 49.0% of patients treated with docetaxel 60 mg/m^2 compared to 55.3% and 65.9% treated with 75 mg/m^2 and 100 mg/m^2 respectively. Discontinuation due to adverse reactions was reported in 5.3% of patients treated with 60 mg/m^2 versus 6.9% and 16.5% for patients treated at 75 mg/m^2 and 100 mg/m^2, respectively. Deaths within 30 days of last treatment occurred in 4.0% of patients treated with 60 mg/m^2 compared to 5.3% and 1.6% for patients treated at 75 mg/m^2 and 100 mg/m^2, respectively.

The following adverse reactions were associated with increasing docetaxel doses: fluid retention (26%, 38%, and 46% at 60 mg/m^2, 75 mg/m^2, and 100 mg/m^2, respectively), thrombocytopenia (7%, 11% and 12%, respectively), neutropenia (92%, 94%, and 97% respectively), febrile neutropenia (5%, 7%, and 14%, respectively), treatment-related grade 3/4 infection (2%, 3%, and 7%, respectively) and anemia (87%, 94%, and 97%, respectively).

Combination therapy with docetaxel in the adjuvant treatment of breast cancer

The following table presents treatment -emergent adverse reactions observed in 744 patients, who were treated with docetaxel 75 mg/m^2 every 3 weeks in combination with doxorubicin and cyclophosphamide (see Table 6).

Table 6 - Clinically Important Treatment -Emergent Adverse Reactions Regardless of Causal Relationship in Patients Receiving Docetaxel in Combination with Doxorubicin and Cyclophosphamide (TAX316)

 | Docetaxel 75 mg/m^2+ Doxorubicin 50 mg/m^2+ Cyclophosphamide 500; mg/m^2 (TAC); n=744; % |  | Fluorouracil 500 mg/m^2+ Doxorubicin 50 mg/m^2+ Cyclophosphamide 500 mg/m^2 (FAC); n=736; %
Adverse Reaction | Any | Grade 3/4 | Any | Grade 3/4
Anemia | 92 | 4 | 72 | 2
Neutropenia | 71 | 66 | 82 | 49
Fever in absence of infection | 47 | 1 | 17 | 0
Infection | 39 | 4 | 36 | 2
Thrombocytopenia | 39 | 2 | 28 | 1
Febrile neutropenia | 25 | N/A | 3 | N/A
Neutropenic infection | 12 | N/A | 6 | N/A
Hypersensitivity reactions | 13 | 1 | 4 | 0
Lymphedema | 4 | 0 | 1 | 0
Fluid Retention [COSTART term and grading system for events related to treatment.]; Peripheral edema; Weight gain | 35; 27; 13 | 1; 0; 0 | 15; 7; 9 | 0; 0; 0
Neuropathy sensory | 26 | 0 | 10 | 0
Neuro-cortical | 5 | 1 | 6 | 1
Neuropathy motor | 4 | 0 | 2 | 0
Neuro-cerebellar | 2 | 0 | 2 | 0
Syncope | 2 | 1 | 1 | 0
Alopecia | 98 | N/A | 97 | N/A
Skin toxicity | 27 | 1 | 18 | 0
Nail disorders | 19 | 0 | 14 | 0
Nausea | 81 | 5 | 88 | 10
Stomatitis | 69 | 7 | 53 | 2
Vomiting | 45 | 4 | 59 | 7
Diarrhea | 35 | 4 | 28 | 2
Constipation | 34 | 1 | 32 | 1
Taste perversion | 28 | 1 | 15 | 0
Anorexia | 22 | 2 | 18 | 1
Abdominal Pain | 11 | 1 | 5 | 0
Amenorrhea | 62 | N/A | 52 | N/A
Cough | 14 | 0 | 10 | 0
Cardiac dysrhythmias | 8 | 0 | 6 | 0
Vasodilatation | 27 | 1 | 21 | 1
Hypotension | 2 | 0 | 1 | 0
Phlebitis | 1 | 0 | 1 | 0
Asthenia | 81 | 11 | 71 | 6
Myalgia | 27 | 1 | 10 | 0
Arthralgia | 19 | 1 | 9 | 0
Lacrimation disorder | 11 | 0 | 7 | 0
Conjunctivitis | 5 | 0 | 7 | 0

Of the 744 patients treated with TAC, 36.3% experienced severe treatment -emergent adverse reactions compared to 26.6% of the 736 patients treated with FAC. Dose reductions due to hematologic toxicity occurred in 1% of cycles in the TAC arm versus 0.1% of cycles in the FAC arm. Six percent of patients treated with TAC discontinued treatment due to adverse reactions, compared to 1.1% treated with FAC; fever in the absence of infection and allergy being the most common reasons for withdrawal among TAC-treated patients. Two patients died in each arm within 30 days of their last study treatment; 1 death per arm was attributed to study drugs.

Fever and Infection

During the treatment period, fever in the absence of infection was seen in 46.5% of TAC-treated patients and in 17.1% of FAC-treated patients. Grade ¾ fever in the absence of infection was seen in 1.3% and 0% of TAC- and FAC-treated patients respectively. Infection was seen in 39.4% of TAC-treated patients compared to 36.3% of FAC-treated patients. Grade 3/4 infection was seen in 3.9% and 2.2% of TAC-treated and FAC-treated patients respectively. There were no septic deaths in either treatment arm during the treatment period.

Gastrointestinal Reactions

In addition to gastrointestinal reactions reflected in the table above, 7 patients in the TAC arm were reported to have colitis/enteritis/large intestine perforation versus one patient in the FAC arm. Five of the 7 TAC-treated patients required treatment discontinuation; no deaths due to these events occurred during the treatment period.

Cardiovascular Reactions

More cardiovascular reactions were reported in the TAC arm versus the FAC arm during the treatment period: arrhythmias, all grades (6.2% vs. 4.9%), and hypotension, all grades (1.9% vs. 0.8%). Twenty-six (26) patients (3.5%) in the TAC arm and 17 patients (2.3%) in the FAC arm developed CHF during the study period. All except one patient in each arm were diagnosed with CHF during the follow-up period. Two (2) patients in TAC arm and 4 patients in FAC arm died due to CHF. The risk of CHF was higher in the TAC arm in the first year, and then was similar in both treatment arms.

Adverse reactions during the follow-up period (median follow-up time of 8 years)

In study TAX316, the most common adverse reactions that started during the treatment period and persisted into the follow-up period in TAC and FAC patients are described below (median follow-up time of 8 years).

Nervous system disorders

In study TAX316, peripheral sensory neuropathy started during the treatment period and persisted into the follow-up period in 84 patients (11.3%) in TAC arm and 15 patients (2%) in FAC arm. At the end of the follow-up period (median follow-up time of 8 years), peripheral sensory neuropathy was observed to be ongoing in 10 patients (1.3%) in TAC arm, and in 2 patients (0.3%) in FAC arm.

Skin and subcutaneous tissue disorders

In study TAX316, alopecia persisting into the follow-up period after the end of chemotherapy was reported in 687 of 744 TAC patients (92.3%) and 645 of 736 FAC patients (87.6%). At the end of the follow-up period (actual median follow-up time of 8 years), alopecia was observed to be ongoing in 29 TAC patients (3.9%) and 16 FAC patients (2.2%).

Reproductive system and breast disorders

In study TAX316, amenorrhea that started during the treatment period and persisted into the follow-up period after the end of chemotherapy was reported in 202 of 744 TAC patients (27.2%) and 125 of 736 FAC patients (17.0%). Amenorrhea was observed to be ongoing at the end of the follow-up period (median follow-up time of 8 years) in 121 of 744 TAC patients (16.3%) and 86 FAC patients (11.7%).

General disorders and administration site conditions

In study TAX316, peripheral edema that started during the treatment period and persisted into the follow-up period after the end of chemotherapy was observed in 119 of 744 TAC patients (16.0%) and 23 of 736 FAC patients (3.1%). At the end of the follow-up period (actual median follow-up time of 8 years), peripheral edema was ongoing in 19 TAC patients (2.6%) and 4 FAC patients (0.5%).

In study TAX316, lymphedema that started during the treatment period and persisted into the follow-up period after the end of chemotherapy was reported in 11 of 744 TAC patients (1.5%) and 1 of 736 FAC patients (0.1%). At the end of the follow-up period (actual median follow-up time of 8 years), lymphedema was observed to be ongoing in 6 TAC patients (0.8%) and 1 FAC patient (0.1%).

In study TAX316, asthenia that started during the treatment period and persisted into the follow-up period after the end of chemotherapy was reported in 236 of 744 TAC patients (31.7%) and 180 of 736 FAC patients (24.5%). At the end of the follow-up period (actual median follow-up time of 8 years), asthenia was observed to be ongoing in 29 TAC patients (3.9%) and 16 FAC patients (2.2%).

Acute Myeloid Leukemia (AML)/Myelodysplastic Syndrome (MDS)

AML occurred in the adjuvant breast cancer trial (TAX316). The cumulative risk of developing treatment-related AML at median follow-up time of 8 years in TAX316 was 0.4% for TAC-treated patients and 0.1% for FAC-treated patients. One TAC patient (0.1%) and 1 FAC patient (0.1%) died due to AML during the follow-up period (median follow-up time of 8 years). Myelodysplastic syndrome occurred in 2 of 744 (0.3%) patients who received TAC and in 1 of 736 (0.1%) patients who received FAC. AML occurs at a higher frequency when these agents are given in combination with radiation therapy.

Lung Cancer

Monotherapy with docetaxel for unresectable, locally advanced or metastatic NSCLC previously treated with platinum-based chemotherapy

Docetaxel 75 mg/m^2: Treatment-emergent adverse drug reactions are shown in Table 7. Included in this table are safety data for a total of 176 patients with non-small cell lung carcinoma and a history of prior treatment with platinum-based chemotherapy who were treated in two randomized, controlled trials. These reactions were described using NCI Common Toxicity Criteria regardless of relationship to study treatment, except for the hematologic toxicities or where otherwise noted.

Table 7 - Treatment -Emergent Adverse Reactions Regardless of Relationship to Treatment in Patients Receiving Docetaxel as Monotherapy for Non-Small Cell Lung Cancer Previously Treated with Platinum-Based Chemotherapy^+

Adverse Reaction | Docetaxel; 75 mg/m^2; n=176; % | Best Supportive Care; n=49; % | Vinorelbine/ Ifosfamide; n=119; %
Neutropenia
Any; Grade 3/4 | 84; 65 | 14; 12 | 83; 57
Leukopenia
Any; Grade 3/4 | 84; 49 | 6; 0 | 89; 43
Thrombocytopenia
Any; Grade 3/4 | 8; 3 | 0; 0 | 8; 2
Anemia
Any; Grade 3/4 | 91; 9 | 55; 12 | 91; 14
Febrile Neutropenia [Febrile Neutropenia: ANC grade 4 with fever >38°C with intravenous antibiotics and/or hospitalization.] | 6 | NA [Not Applicable.] | 1
Infection
Any; Grade 3/4 | 34; 10 | 29; 6 | 30; 9
Treatment Related Mortality | 3 | NA | 3
Hypersensitivity Reactions
Any; Grade 3/4 | 6; 3 | 0; 0 | 1; 0
Fluid Retention
Any; Severe | 34; 3 | ND [Not Done.] | 23; 3
Neurosensory
Any; Grade 3/4 | 23; 2 | 14; 6 | 29; 5
Neuromotor
Any; Grade 3/4 | 16; 5 | 8; 6 | 10; 3
Skin
Any; Grade 3/4 | 20; 1 | 6; 2 | 17; 1
Gastrointestinal
Nausea
Any | 34 | 31 | 31
Grade 3/4 | 5 | 4 | 8
Vomiting
Any | 22 | 27 | 22
Grade 3/4 | 3 | 2 | 6
Diarrhea
Any | 23 | 6 | 12
Grade 3/4 | 3 | 0 | 4
Alopecia | 56 | 35 | 50
Asthenia
Any | 53 | 57 | 54
Severe [COSTART term and grading system.] | 18 | 39 | 23
Stomatitis
Any | 26 | 6 | 8
Grade 3/4 | 2 | 0 | 1
Pulmonary
Any | 41 | 49 | 45
Grade 3/4 | 21 | 29 | 19
Nail Disorder
Any | 11 | 0 | 2
Severe | 1 | 0 | 0
Myalgia
Any | 6 | 0 | 3
Severe | 0 | 0 | 0
Arthralgia
Any | 3 | 2 | 2
Severe | 0 | 0 | 1
Taste Perversion
Any | 6 | 0 | 0
Severe | 1 | 0 | 0
^+Normal Baseline LFTs: Transaminases ≤1.5 times ULN or alkaline phosphatase ≤2.5 times ULN or isolated elevations of transaminases or alkaline phosphatase up to 5 times ULN.

Combination therapy with docetaxel in chemotherapy-naive advanced unresectable or metastatic NSCLC

Table 8 presents safety data from two arms of an open label, randomized controlled trial (TAX326) that enrolled patients with unresectable stage IIIB or IV non-small cell lung cancer and no history of prior chemotherapy. Adverse reactions were described using the NCI Common Toxicity Criteria except where otherwise noted.

Table 8 - Adverse Reactions Regardless of Relationship to Treatment in Chemotherapy-Naive Advanced Non-Small Cell Lung Cancer Patients Receiving Docetaxel in Combination with Cisplatin

Adverse Reaction | Docetaxel 75 mg/m^2 + Cisplatin 75 mg/m^2; n=406; % | Vinorelbine 25 mg/m^2 + Cisplatin 100 mg/m^2; n=396; %
Neutropenia
Any | 91 | 90
Grade 3/4 | 74 | 78
Febrile Neutropenia | 5 | 5
Thrombocytopenia
Any | 15 | 15
Grade 3/4 | 3 | 4
Anemia
Any | 89 | 94
Grade 3/4 | 7 | 25
Infection
Any | 35 | 37
Grade 3/4 | 8 | 8
Fever in absence of infection
Any | 33 | 29
Grade 3/4 | <1 | 1
Hypersensitivity Reaction [Replaces NCI term "Allergy".]
Any | 12 | 4
Grade 3/4 | 3 | <1
Fluid Retention [COSTART term and grading system.]
Any | 54 | 42
All severe or life-threatening events | 2 | 2
Pleural effusion
Any | 23 | 22
All severe or life-threatening events | 2 | 2
Peripheral edema
Any | 34 | 18
All severe or life-threatening events | <1 | <1
Weight gain
Any | 15 | 9
All severe or life-threatening events | <1 | <1
Neurosensory
Any | 47 | 42
Grade 3/4 | 4 | 4
Neuromotor
Any | 19 | 17
Grade 3/4 | 3 | 6
Skin
Any | 16 | 14
Grade 3/4 | <1 | 1
Nausea
Any | 72 | 76
Grade 3/4 | 10 | 17
Vomiting
Any | 55 | 61
Grade 3/4 | 8 | 16
Diarrhea
Any | 47 | 25
Grade 3/4 | 7 | 3
Anorexia
Any | 42 | 40
All severe or life-threatening events | 5 | 5
Stomatitis
Any | 24 | 21
Grade 3/4 | 2 | 1
Alopecia
Any | 75 | 42
Grade 3 | <1 | 0
Asthenia
Any | 74 | 75
All severe or life-threatening events | 12 | 14
Nail Disorder
Any | 14 | <1
All severe events | <1 | 0
Myalgia
Any | 18 | 12
All severe events | <1 | <1

Deaths within 30 days of last study treatment occurred in 31 patients (7.6%) in the docetaxel+cisplatin arm and 37 patients (9.3%) in the vinorelbine+cisplatin arm. Deaths within 30 days of last study treatment attributed to study drug occurred in 9 patients (2.2%) in the docetaxel+cisplatin arm and 8 patients (2%) in the vinorelbine+cisplatin arm.

The second comparison in the study, vinorelbine+cisplatin versus docetaxel+carboplatin (which did not demonstrate a superior survival associated with docetaxel, [see Clinical Studies (14.3)] demonstrated a higher incidence of thrombocytopenia, diarrhea, fluid retention, hypersensitivity reactions, skin toxicity, alopecia and nail changes on the docetaxel+carboplatin arm, while a higher incidence of anemia, neurosensory toxicity, nausea, vomiting, anorexia and asthenia was observed on the vinorelbine+cisplatin arm.

Prostate Cancer

Combination therapy with docetaxel in patients with prostate cancer

The following data are based on the experience of 332 patients, who were treated with docetaxel 75 mg/m^2 every 3 weeks in combination with prednisone 5 mg orally twice daily (see Table 9).

Table 9 - Clinically Important Treatment-Emergent Adverse Reactions (Regardless of Relationship) in Patients with Prostate Cancer Who Received Docetaxel in Combination with Prednisone (TAX327)

 | Docetaxel 75 mg/m^2 every 3 weeks + prednisone 5 mg twice daily; n=332; % |  | Mitoxantrone 12 mg/m^2 every 3 weeks + prednisone 5 mg twice daily; n=335; %
Adverse Reaction | Any | Grade 3/4 | Any | Grade 3/4
Anemia | 67 | 5 | 58 | 2
Neutropenia | 41 | 32 | 48 | 22
Thrombocytopenia | 3 | 1 | 8 | 1
Febrile Neutropenia | 3 | N/A | 2 | N/A
Infection | 32 | 6 | 20 | 4
Epistaxis | 6 | 0 | 2 | 0
Allergic Reactions | 8 | 1 | 1 | 0
Fluid Retention [Related to treatment.]; Weight Gain; Peripheral Edema | 24; 8; 18 | 1; 0; 0 | 5; 3; 2 | 0; 0; 0
Neuropathy Sensory | 30 | 2 | 7 | 0
Neuropathy Motor | 7 | 2 | 3 | 1
Rash/Desquamation | 6 | 0 | 3 | 1
Alopecia | 65 | N/A | 13 | N/A
Nail Changes | 30 | 0 | 8 | 0
Nausea | 41 | 3 | 36 | 2
Diarrhea | 32 | 2 | 10 | 1
Stomatitis/Pharyngitis | 20 | 1 | 8 | 0
Taste Disturbance | 18 | 0 | 7 | 0
Vomiting | 17 | 2 | 14 | 2
Anorexia | 17 | 1 | 14 | 0
Cough | 12 | 0 | 8 | 0
Dyspnea | 15 | 3 | 9 | 1
Cardiac left ventricular function | 10 | 0 | 22 | 1
Fatigue | 53 | 5 | 35 | 5
Myalgia | 15 | 0 | 13 | 1
Tearing | 10 | 1 | 2 | 0
Arthralgia | 8 | 1 | 5 | 1

Gastric Cancer

Combination therapy with docetaxel injection in gastric adenocarcinoma

Data in the following table are based on the experience of 221 patients with advanced gastric adenocarcinoma and no history of prior chemotherapy for advanced disease, who were treated with docetaxel injection 75 mg/m^2 in combination with cisplatin and fluorouracil (see Table 10).

Table 10 - Clinically Important Treatment-Emergent Adverse Reactions Regardless of Relationship to Treatment in the Gastric Cancer Study

 | Docetaxel Injection 75 mg/m^2 + cisplatin 75 mg/m^2 + fluorouracil 750 mg/m^2; n=221 |  | Cisplatin 100 mg/m^2 + fluorouracil 1000 mg/m^2 n=224
Adverse Reaction | Any; % | Grade 3/4; % | Any; % | Grade 3/4; %
Anemia | 97 | 18 | 93 | 26
Neutropenia | 96 | 82 | 83 | 57
Fever in the absence of infection | 36 | 2 | 23 | 1
Thrombocytopenia | 26 | 8 | 39 | 14
Infection | 29 | 16 | 23 | 10
Febrile neutropenia | 16 | N/A | 5 | N/A
Neutropenic infection | 16 | N/A | 10 | N/A
Allergic reactions | 10 | 2 | 6 | 0
Fluid retention [Related to treatment.] | 15 | 0 | 4 | 0
Edema | 13 | 0 | 3 | 0
Lethargy | 63 | 21 | 58 | 18
Neurosensory | 38 | 8 | 25 | 3
Neuromotor | 9 | 3 | 8 | 3
Dizziness | 16 | 5 | 8 | 2
Alopecia | 67 | 5 | 41 | 1
Rash/itch | 12 | 1 | 9 | 0
Nail changes | 8 | 0 | 0 | 0
Skin desquamation | 2 | 0 | 0 | 0
Nausea | 73 | 16 | 76 | 19
Vomiting | 67 | 15 | 73 | 19
Anorexia | 51 | 13 | 54 | 12
Stomatitis | 59 | 21 | 61 | 27
Diarrhea | 78 | 20 | 50 | 8
Constipation | 25 | 2 | 34 | 3
Esophagitis/dysphagia/ odynophagia | 16 | 2 | 14 | 5
Gastrointestinal pain/cramping | 11 | 2 | 7 | 3
Cardiac dysrhythmias | 5 | 2 | 2 | 1
Myocardial ischemia | 1 | 0 | 3 | 2
Tearing | 8 | 0 | 2 | 0
Altered hearing | 6 | 0 | 13 | 2
Clinically important treatment-emergent adverse reactions were determined based upon frequency, severity, and clinical impact of the adverse reaction.

Head and Neck Cancer

Combination therapy with docetaxel injection in head and neck cancer

Table 11 summarizes the safety data obtained from patients that received induction chemotherapy with docetaxel injection 75 mg/m^2 in combination with cisplatin and fluorouracil followed by radiotherapy (TAX323; 174 patients) or chemoradiotherapy (TAX324; 251 patients). The treatment regimens are described in Section 14.6.

Table 11 - Clinically Important Treatment-Emergent Adverse Reactions (Regardless of Relationship) in Patients with SCCHN Receiving Induction Chemotherapy with Docetaxel Injection in Combination with Cisplatin and Fluorouracil Followed by Radiotherapy (TAX323) or Chemoradiotherapy (TAX324)

 | TAX323; (n=355) |  |  |  | TAX324; (n=494)
 | Docetaxel Injection; arm (n=174) |  | Comparator arm (n=181) |  | Docetaxel Injection; arm (n=251) |  | Comparator arm (n=243)
Adverse Reaction; (by Body System) | Any; % | Grade; 3/4 % | Any; % | Grade; 3/4 % | Any; % | Grade; 3/4 % | Any; % | Grade; 3/4 %
Neutropenia | 93 | 76 | 87 | 53 | 95 | 84 | 84 | 56
Anemia | 89 | 9 | 88 | 14 | 90 | 12 | 86 | 10
Thrombocytopenia | 24 | 5 | 47 | 18 | 28 | 4 | 31 | 11
Infection | 27 | 9 | 26 | 8 | 23 | 6 | 28 | 5
Febrile neutropenia [Febrile neutropenia: grade ≥2 fever concomitant with grade 4 neutropenia requiring intravenous antibiotics and/or hospitalization.] | 5 | N/A | 2 | N/A | 12 | N/A | 7 | N/A
Neutropenic infection | 14 | N/A | 8 | N/A | 12 | N/A | 8 | N/A
Cancer pain | 21 | 5 | 16 | 3 | 17 | 9 | 20 | 11
Lethargy | 41 | 3 | 38 | 3 | 61 | 5 | 56 | 10
Fever in the absence of infection | 32 | 1 | 37 | 0 | 30 | 4 | 28 | 3
Myalgia | 10 | 1 | 7 | 0 | 7 | 0 | 7 | 2
Weight loss | 21 | 1 | 27 | 1 | 14 | 2 | 14 | 2
Allergy | 6 | 0 | 3 | 0 | 2 | 0 | 0 | 0
Fluid retention [Related to treatment.]; Edema only; Weight gain only | 20; 13; 6 | 0; 0; 0 | 14; 7; 6 | 1; 0; 0 | 13; 12; 0 | 1; 1; 0 | 7; 6; 1 | 2; 1; 0
Dizziness | 2 | 0 | 5 | 1 | 16 | 4 | 15 | 2
Neurosensory | 18 | 1 | 11 | 1 | 14 | 1 | 14 | 0
Altered hearing | 6 | 0 | 10 | 3 | 13 | 1 | 19 | 3
Neuromotor | 2 | 1 | 4 | 1 | 9 | 0 | 10 | 2
Alopecia | 81 | 11 | 43 | 0 | 68 | 4 | 44 | 1
Rash/itch | 12 | 0 | 6 | 0 | 20 | 0 | 16 | 1
Dry skin | 6 | 0 | 2 | 0 | 5 | 0 | 3 | 0
Desquamation | 4 | 1 | 6 | 0 | 2 | 0 | 5 | 0
Nausea | 47 | 1 | 51 | 7 | 77 | 14 | 80 | 14
Stomatitis | 43 | 4 | 47 | 11 | 66 | 21 | 68 | 27
Vomiting | 26 | 1 | 39 | 5 | 56 | 8 | 63 | 10
Diarrhea | 33 | 3 | 24 | 4 | 48 | 7 | 40 | 3
Constipation | 17 | 1 | 16 | 1 | 27 | 1 | 38 | 1
Anorexia | 16 | 1 | 25 | 3 | 40 | 12 | 34 | 12
Esophagitis/dysphagia/ Odynophagia | 13 | 1 | 18 | 3 | 25 | 13 | 26 | 10
Taste, sense of smell altered | 10 | 0 | 5 | 0 | 20 | 0 | 17 | 1
Gastrointestinal pain/cramping | 8 | 1 | 9 | 1 | 15 | 5 | 10 | 2
Heartburn | 6 | 0 | 6 | 0 | 13 | 2 | 13 | 1
Gastrointestinal bleeding | 4 | 2 | 0 | 0 | 5 | 1 | 2 | 1
Cardiac dysrhythmia | 2 | 2 | 2 | 1 | 6 | 3 | 5 | 3
Venous [Includes superficial and deep vein thrombosis and pulmonary embolism.] | 3 | 2 | 6 | 2 | 4 | 2 | 5 | 4
Ischemia myocardial | 2 | 2 | 1 | 0 | 2 | 1 | 1 | 1
Tearing | 2 | 0 | 1 | 0 | 2 | 0 | 2 | 0
Conjunctivitis | 1 | 0 | 1 | 0 | 1 | 0 | 0.4 | 0
Clinically important treatment-emergent adverse reactions based upon frequency, severity, and clinical impact.

6.2 Postmarketing Experience

The following adverse reactions have been identified from clinical trials and/or postmarketing surveillance. Because these reactions are reported from a population of uncertain size, it is not always possible to reliably estimate their frequency or establish a causal relationship to drug exposure.

Body as a whole: diffuse pain, chest pain, radiation recall phenomenon, injection site recall reaction (recurrence of skin reaction at a site of previous extravasation following administration of docetaxel at a different site) at the site of previous extravasation.

Cardiovascular: atrial fibrillation, deep vein thrombosis, ECG abnormalities, thrombophlebitis, pulmonary embolism, syncope, tachycardia, myocardial infarction. Ventricular arrhythmia, including ventricular tachycardia, in patients treated with docetaxel in combination regimens including doxorubicin, 5-fluorouracil and/or cyclophosphamide, may be associated with fatal outcome.

Cutaneous: cutaneous lupus erythematosus, bullous eruptions such as erythema multiforme and severe cutaneous adverse reactions (SCARs) such as Stevens-Johnson syndrome, toxic epidermal necrolysis, and acute generalized exanthematous pustulosis, scleroderma-like changes (usually preceded by peripheral lymphedema), severe palmar-plantar erythrodysesthesia, and permanent alopecia.

Gastrointestinal: enterocolitis, including colitis, ischemic colitis, and neutropenic enterocolitis, which may be fatal. Abdominal pain, anorexia, constipation, duodenal ulcer, esophagitis, gastrointestinal hemorrhage, gastrointestinal perforation, intestinal obstruction, ileus, and dehydration as a consequence of gastrointestinal events.

Hearing: ototoxicity, hearing disorders and/or hearing loss, including during use with other ototoxic drugs.

Hematologic: bleeding episodes, disseminated intravascular coagulation (DIC), often in association with sepsis or multiorgan failure.

Hepatic: hepatitis, sometimes fatal, primarily in patients with pre-existing liver disorders.

Hypersensitivity: anaphylactic shock with fatal outcome in patients who received premedication. Severe hypersensitivity reactions with fatal outcome with docetaxel in patients who previously experienced hypersensitivity reactions to paclitaxel.

Metabolism and Nutrition Disorders: electrolyte imbalance, including hyponatremia, hypokalemia, hypomagnesemia, and hypocalcemia. Tumor lysis syndrome, sometimes fatal.

Neurologic: confusion, seizures or transient loss of consciousness, sometimes appearing during the infusion of the drug.

Ophthalmologic: conjunctivitis, lacrimation or lacrimation with or without conjunctivitis, cystoid macular edema (CME). Excessive tearing which may be attributable to lacrimal duct obstruction. Transient visual disturbances (flashes, flashing lights, scotomata) typically occurring during drug infusion and reversible upon discontinuation of the infusion, in association with hypersensitivity reactions.

Respiratory: dyspnea, acute pulmonary edema, acute respiratory distress syndrome/pneumonitis, interstitial lung disease, interstitial pneumonia, respiratory failure, and pulmonary fibrosis, which may be fatal. Radiation pneumonitis in patients receiving concomitant radiotherapy.

Renal: renal insufficiency and renal failure, the majority of cases were associated with concomitant nephrotoxic drugs.

Second primary malignancies: second primary malignancies, including AML, MDS, NHL, and renal cancer [see Warnings and Precautions (5.7)].

Musculoskeletal disorder: myositis.

7. DRUG INTERACTIONS

Docetaxel is a CYP3A4 substrate. In vitro studies have shown that the metabolism of docetaxel may be modified by the concomitant administration of compounds that induce, inhibit, or are metabolized by cytochrome P450 3A4.

In vivo studies showed that the exposure of docetaxel increased 2.2-fold when it was co-administered with ketoconazole, a potent inhibitor of CYP3A4. Protease inhibitors, particularly ritonavir, may increase the exposure of docetaxel. Concomitant use of Docetaxel Injection and drugs that inhibit CYP3A4 may increase exposure to docetaxel and should be avoided. In patients receiving treatment with Docetaxel Injection, close monitoring for toxicity and a Docetaxel Injection dose reduction could be considered if systemic administration of a potent CYP3A4 inhibitor cannot be avoided [see Dosage and Administration (2.7), Clinical Pharmacology (12.3)].

8. USE IN SPECIFIC POPULATIONS

8.1 Pregnancy

Risk Summary

Based on findings in animal reproduction studies and its mechanism of action, Docetaxel Injection can cause fetal harm when administered to a pregnant woman [see Clinical Pharmacology (12.1)]. Available data from case reports in the literature and pharmacovigilance with docetaxel use in pregnant women are not sufficient to inform the drug-associated risk of major birth defects, miscarriage, or adverse maternal or fetal outcomes. Docetaxel Injection contains alcohol which can interfere with neurobehavioral development [see Clinical Considerations]. In animal reproductive studies, administration of docetaxel to pregnant rats and rabbits during the period of organogenesis caused an increased incidence of embryo-fetal toxicities, including intrauterine mortality, at doses as low as 0.02 and 0.003 times the recommended human dose based on body surface area, respectively [see Data]. Advise pregnant women and females of reproductive potential of the potential risk to a fetus.

The estimated background risk of major birth defects and miscarriage for the indicated populations is unknown. All pregnancies have a background risk of birth defect, miscarriage, or other adverse outcomes. In the U.S. general population, the estimated background risk of major birth defects and miscarriage in clinically recognized pregnancies is 2% to 4% and 15% to 20%, respectively.

Clinical Considerations

Docetaxel Injection contains alcohol [see Warnings and Precautions (5.13)]. Published studies have demonstrated that alcohol is associated with fetal harm including central nervous system abnormalities, behavioral disorders, and impaired intellectual development.

Data

Animal data

Intravenous administration of ≥0.3 and 0.03 mg/kg/day docetaxel to pregnant rats and rabbits, respectively, during the period of organogenesis caused an increased incidence of intrauterine mortality, resorptions, reduced fetal weights, and fetal ossification delays. Maternal toxicity was also observed at these doses, which were approximately 0.02 and 0.003 times the daily maximum recommended human dose based on body surface area, respectively.

8.2 Lactation

Risk Summary

There is no information regarding the presence of docetaxel in human milk, or on its effects on milk production or the breastfed child. No lactation studies in animals have been conducted. Because of the potential for serious adverse reactions in a breastfed child, advise women not to breastfeed during treatment with Docetaxel Injection and for 1 week after the last dose.

8.3 Females and Males of Reproductive Potential

Based on findings in animals, Docetaxel Injection can cause fetal harm when administered to a pregnant woman [see Use in Specific Populations (8.1)].

Pregnancy Testing

Verify pregnancy status in females of reproductive potential prior to initiating Docetaxel Injection.

Contraception

Females

Based on genetic toxicity findings, advise females of reproductive potential to use effective contraception during treatment and for 2 months after the last dose of Docetaxel Injection.

Males

Based on genetic toxicity findings, advise male patients with female partners of reproductive potential to use effective contraception during treatment and for 4 months after the last dose of Docetaxel Injection.

Infertility

Based on findings in animal studies, Docetaxel Injection may impair fertility in males of reproductive potential [see Nonclinical Toxicology (13.1)].

8.4 Pediatric Use

The alcohol content of Docetaxel Injection should be taken into account when given to pediatric patients [see Warnings and Precautions (5.13)].

The efficacy of docetaxel in pediatric patients as monotherapy or in combination has not been established. The overall safety profile of docetaxel in pediatric patients receiving monotherapy or TCF was consistent with the known safety profile in adults.

Docetaxel has been studied in a total of 289 pediatric patients: 239 in 2 trials with monotherapy and 50 in combination treatment with cisplatin and 5-fluorouracil (TCF).

Docetaxel Monotherapy

Docetaxel monotherapy was evaluated in a dose-finding phase 1 trial in 61 pediatric patients (median age 12.5 years, range 1-22 years) with a variety of refractory solid tumors. The recommended dose was 125 mg/m^2 as a 1-hour intravenous infusion every 21 days. The primary dose limiting toxicity was neutropenia.

The recommended dose for docetaxel monotherapy was evaluated in a phase 2 single-arm trial in 178 pediatric patients (median age 12 years, range 1-26 years) with a variety of recurrent/refractory solid tumors. Efficacy was not established with tumor response rates ranging from one complete response (CR) (0.6%) in a patient with undifferentiated sarcoma to four partial responses (2.2%) seen in one patient each with Ewing Sarcoma, neuroblastoma, osteosarcoma, and squamous cell carcinoma.

Docetaxel in Combination

Docetaxel was studied in combination with cisplatin and 5-fluorouracil (TCF) versus cisplatin and 5-fluorouracil (CF) for the induction treatment of nasopharyngeal carcinoma (NPC) in pediatric patients prior to chemoradiation consolidation. Seventy-five patients (median age 16 years, range 9 to 21 years) were randomized (2:1) to docetaxel (75 mg/m^2) in combination with cisplatin (75 mg/m^2) and 5-fluorouracil (750 mg/m^2) (TCF) or to cisplatin (80 mg/m^2) and 5-fluorouracil (1000 mg/m^2/day) (CF). The primary endpoint was the CR rate following induction treatment of NPC. One patient out of 50 in the TCF group (2%) had a complete response while none of the 25 patients in the CF group had a complete response.

Pharmacokinetics

Pharmacokinetic parameters for docetaxel were determined in 2 pediatric solid tumor trials. Following docetaxel administration at 55 mg/m^2 to 235 mg/m^2 in a 1-hour intravenous infusion every 3 -weeks in 25 patients aged 1 to 20 years (median 11 years), docetaxel clearance was 17.3±10.9 L/h/m^2.

Docetaxel was administered in combination with cisplatin and 5-fluorouracil (TCF), at dose levels of 75 mg/m^2 in a 1-hour intravenous infusion day 1 in 28 patients aged 10 to 21 years (median 16 years, 17 patients were older than 16). Docetaxel clearance was 17.9±8.75 L/h/m^2, corresponding to an AUC of 4.20±2.57 µg•h/mL.

In summary, the body surface area adjusted clearance of docetaxel monotherapy and TCF combination in children were comparable to those in adults [see Clinical Pharmacology (12.3)].

8.5 Geriatric Use

In general, dose selection for an elderly patient should be cautious, reflecting the greater frequency of decreased hepatic, renal, or cardiac function and of concomitant disease or other drug therapy in elderly patients.

Non-Small Cell Lung Cancer

In a study conducted in chemotherapy-naive patients with NSCLC (TAX326), 148 patients (36%) in the docetaxel+cisplatin group were 65 years of age or greater. There were 128 patients (32%) in the vinorelbine+cisplatin group 65 years of age or greater. In the docetaxel+cisplatin group, patients less than 65 years of age had a median survival of 10.3 months (95% CI: 9.1 months, 11.8 months) and patients 65 years or older had a median survival of 12.1 months (95% CI: 9.3 months, 14 months). In patients 65 years of age or greater treated with docetaxel+cisplatin, diarrhea (55%), peripheral edema (39%) and stomatitis (28%) were observed more frequently than in the vinorelbine+cisplatin group (diarrhea 24%, peripheral edema 20%, stomatitis 20%). Patients treated with docetaxel+cisplatin who were 65 years of age or greater were more likely to experience diarrhea (55%), infections (42%), peripheral edema (39%) and stomatitis (28%) compared to patients less than the age of 65 administered the same treatment (43%, 31%, 31% and 21%, respectively).

When docetaxel was combined with carboplatin for the treatment of chemotherapy-naive, advanced non-small cell lung carcinoma, patients 65 years of age or greater (28%) experienced higher frequency of infection compared to similar patients treated with docetaxel+cisplatin, and a higher frequency of diarrhea, infection and peripheral edema than elderly patients treated with vinorelbine+cisplatin.

Prostate Cancer

Of the 333 patients treated with docetaxel every three weeks plus prednisone in the prostate cancer study (TAX327), 209 patients were 65 years of age or greater and 68 patients were older than 75 years. In patients treated with docetaxel every three weeks, the following treatment -emergent adverse reactions occurred at rates ≥10% higher in patients 65 years of age or greater compared to younger patients: anemia (71% vs. 59%), infection (37% vs. 24%), nail changes (34% vs. 23%), anorexia (21% vs. 10%), weight loss (15% vs. 5%), respectively.

Breast Cancer

In the adjuvant breast cancer trial (TAX316), docetaxel in combination with doxorubicin and cyclophosphamide was administered to 744 patients of whom 48 (6%) were 65 years of age or greater. The number of elderly patients who received this regimen was not sufficient to determine whether there were differences in safety and efficacy between elderly and younger patients.

Gastric Cancer

Among the 221 patients treated with docetaxel injection in combination with cisplatin and fluorouracil in the gastric cancer study, 54 were 65 years of age or older and 2 patients were older than 75 years. In this study, the number of patients who were 65 years of age or older was insufficient to determine whether they respond differently from younger patients. However, the incidence of serious adverse reactions was higher in the elderly patients compared to younger patients. The incidence of the following adverse reactions (all grades, regardless of relationship): lethargy, stomatitis, diarrhea, dizziness, edema, febrile neutropenia/neutropenic infection occurred at rates ≥10% higher in patients who were 65 years of age or older compared to younger patients. Elderly patients treated with TCF should be closely monitored.

Head and Neck Cancer

Among the 174 and 251 patients who received the induction treatment with docetaxel injection in combination with cisplatin and fluorouracil (TPF) for SCCHN in the TAX323 and TAX324 studies, 18 (10%) and 32 (13%) of the patients were 65 years of age or older, respectively.

These clinical studies of docetaxel injection in combination with cisplatin and fluorouracil in patients with SCCHN did not include sufficient numbers of patients aged 65 and over to determine whether they respond differently from younger patients. Other reported clinical experience with this treatment regimen has not identified differences in responses between elderly and younger patients.

8.6 Hepatic Impairment

Avoid docetaxel in patients with bilirubin >ULN and patients with AST and/or ALT >1.5 x ULN concomitant with alkaline phosphatase >2.5 x ULN [see Boxed Warning, Warnings and Precautions (5.2), Clinical Pharmacology (12.3)].

The alcohol content of Docetaxel Injection should be taken into account when given to patients with hepatic impairment [see Warnings and Precautions (5.13)].

10. OVERDOSAGE

There is no known antidote for Docetaxel Injection overdosage. In case of overdosage, the patient should be kept in a specialized unit where vital functions can be closely monitored. Anticipated complications of overdosage include: bone marrow suppression, peripheral neurotoxicity, and mucositis. Patients should receive therapeutic G-CSF as soon as possible after discovery of overdose. Other appropriate symptomatic measures should be taken, as needed.

In two reports of overdose, one patient received 150 mg/m^2 and the other received 200 mg/m^2 as 1-hour infusions. Both patients experienced severe neutropenia, mild asthenia, cutaneous reactions, and mild paresthesia, and recovered without incident. In mice, lethality was observed following single intravenous doses that were ≥154 mg/kg (about 4.5 times the human dose of 100 mg/m^2 on a mg/m^2 basis); neurotoxicity associated with paralysis, non-extension of hind limbs, and myelin degeneration was observed in mice at 48 mg/kg (about 1.5 times the human dose of 100 mg/m^2 basis). In male and female rats, lethality was observed at a dose of 20 mg/kg (comparable to the human dose of 100 mg/m^2 on a mg/m^2 basis) and was associated with abnormal mitosis and necrosis of multiple organs.

11. DESCRIPTION

Docetaxel is an antineoplastic agent belonging to the taxoid family. It is prepared by semisynthesis beginning with a precursor extracted from the renewable needle biomass of yew plants. The chemical name for docetaxel is (2R,3S)-N-carboxy-3-phenylisoserine, N-tert-butyl ester, 13-ester with 5β-20-epoxy-1,2α,4,7β,10β,13α-hexahydroxytax-11-en-9-one 4-acetate 2-benzoate. Docetaxel has the following structural formula:

Docetaxel is a white to almost-white powder with an empirical formula of C43H53NO14, and a molecular weight of 807.88. It is highly lipophilic and practically insoluble in water.

Docetaxel Injection is a clear, colorless to pale yellow solution. Docetaxel Injection is sterile, non-pyrogenic, and is available in multiple-dose vials, supplied as 20 mg/2 mL, 80 mg/8 mL and 160 mg/16 mL.

Each mL of Docetaxel Injection contains 10 mg docetaxel, 275.9 mg alcohol 96% (v/v), 4 mg citric acid, 648 mg polyethylene glycol 300, and 80 mg polysorbate 80.

12. CLINICAL PHARMACOLOGY

12.1 Mechanism of Action

Docetaxel is an antineoplastic agent that acts by disrupting the microtubular network in cells that is essential for mitotic and interphase cellular functions. Docetaxel binds to free tubulin and promotes the assembly of tubulin into stable microtubules while simultaneously inhibiting their disassembly. This leads to the production of microtubule bundles without normal function and to the stabilization of microtubules, which results in the inhibition of mitosis in cells. Docetaxel's binding to microtubules does not alter the number of protofilaments in the bound microtubules, a feature which differs from most spindle poisons currently in clinical use.

12.3 Pharmacokinetics

Absorption The pharmacokinetics of docetaxel has been evaluated in cancer patients after administration of 20 mg/m^2 to 115 mg/m^2 in phase 1 studies. The area under the curve (AUC) was dose proportional following doses of 70 mg/m^2 to 115 mg/m^2 with infusion times of 1 to 2 hours. Docetaxel's pharmacokinetic profile is consistent with a three-compartment pharmacokinetic model, with initial rapid distribution phase and the late (terminal) phase.

Distribution Mean steady state volume of distribution was 113 L. Docetaxel is approximately 94% protein bound in vitro, mainly to α1-acid glycoprotein, albumin, and lipoproteins. In three cancer patients, the in vitro binding to plasma proteins was approximately 97%. Dexamethasone does not affect the protein binding of docetaxel.

Elimination

With extended plasma sampling up to 8 to 22 days post infusion, the estimated mean total body clearance was 18 L/h/m^2 (range of means: 14 to 23) and mean terminal elimination half-life was 116 hours (range of means: 92 to 135).

Metabolism

Docetaxel is metabolized by the CYP3A4 isoenzyme in vitro [see Drug Interactions (7)].

Excretion In three cancer patients urinary and fecal excretion accounted for approximately 6% and 75% of the administered radioactivity, respectively, within 7 days. About 80% of the radioactivity recovered in feces was excreted during the first 48 hours as 1 major and 3 minor metabolites with less than 8% as unchanged drug.

Specific Populations

Effect of Age: A population pharmacokinetic analysis was carried out after docetaxel treatment of 535 patients dosed at 100 mg/m^2. Pharmacokinetic parameters estimated by this analysis were very close to those estimated from phase 1 studies. The pharmacokinetics of docetaxel was not influenced by age.

Effect of Gender: The population pharmacokinetics analysis described above also indicated that gender did not influence the pharmacokinetics of docetaxel.

Hepatic Impairment: The population pharmacokinetic analysis described above indicated that in patients with clinical chemistry data suggestive of mild to moderate liver impairment (AST and/or ALT >1.5 times ULN concomitant with alkaline phosphatase >2.5 times ULN), total body clearance was lowered by an average of 27%, resulting in a 38% increase in systemic exposure (AUC). This average, however, includes a substantial range and there is, at present, no measurement that would allow recommendation for dose adjustment in such patients. Patients with combined abnormalities of transaminase and alkaline phosphatase should not be treated with Docetaxel Injection. Patients with severe hepatic impairment have not been studied [see Warnings and Precautions (5.2), Use in Specific Populations (8.6)].

Effect of Race: Mean total body clearance for Japanese patients dosed at the range of 10 mg/m^2 to 90 mg/m^2 was similar to that of European/American populations dosed at 100 mg/m^2, suggesting no significant difference in the elimination of docetaxel in the two populations.

Drug Interaction Studies

Effect of Ketoconazole: The effect of ketoconazole (a strong CYP3A4 inhibitor) on the pharmacokinetics of docetaxel was investigated in 7 cancer patients. Patients were randomized to receive either docetaxel (100 mg/m^2 intravenous) alone or docetaxel (10 mg/m^2 intravenous) in combination with ketoconazole (200 mg orally once daily for 3 days) in a crossover design with a 3-week washout period. The results of this study indicated that the mean dose-normalized AUC of docetaxel was increased 2.2-fold and its clearance was reduced by 49% when docetaxel was co-administered with ketoconazole [see Dosage and Administration (2.7), Drug Interactions (7)].

Effect of Combination Therapies:

- Dexamethasone: Docetaxel total body clearance was not modified by pretreatment with dexamethasone.
- Cisplatin: Clearance of docetaxel in combination therapy with cisplatin was similar to that previously observed following monotherapy with docetaxel. The pharmacokinetic profile of cisplatin in combination therapy with docetaxel was similar to that observed with cisplatin alone.
- Cisplatin and Fluorouracil: The combined administration of docetaxel, cisplatin and fluorouracil in 12 patients with solid tumors had no influence on the pharmacokinetics of each individual drug.
- Prednisone: A population pharmacokinetic analysis of plasma data from 40 patients with metastatic castration-resistant prostate cancer indicated that docetaxel systemic clearance in combination with prednisone is similar to that observed following administration of docetaxel alone.
- Cyclophosphamide and Doxorubicin: A study was conducted in 30 patients with advanced breast cancer to determine the potential for drug-drug interactions between docetaxel (75 mg/m^2), doxorubicin (50 mg/m^2), and cyclophosphamide (500 mg/m^2) when administered in combination. The co-administration of docetaxel had no effect on the pharmacokinetics of doxorubicin and cyclophosphamide when the three drugs were given in combination compared to co-administration of doxorubicin and cyclophosphamide only. In addition, doxorubicin and cyclophosphamide had no effect on docetaxel plasma clearance when the three drugs were given in combination compared to historical data for docetaxel monotherapy.

13. NONCLINICAL TOXICOLOGY

13.1 Carcinogenesis, Mutagenesis, Impairment of Fertility

Carcinogenicity studies with docetaxel have not been performed.

Docetaxel was genotoxic by an aneugenic mechanism in the in vitro chromosome aberration test in CHO-K1 cells and in the in vivo micronucleus test in mice administered doses of 0.39 to 1.56 mg/kg (about 1/60th to 1/15th the recommended human dose on a mg/m^2 basis). Docetaxel was not mutagenic in the Ames test or the CHO/HGPRT gene mutation assays.

Docetaxel did not reduce fertility in rats when administered in multiple intravenous doses of up to 0.3 mg/kg (about 1/50th the recommended human dose on a mg/m^2 basis), but decreased testicular weights were reported. This correlates with findings of a 10-cycle toxicity study (dosing once every 21 days for 6 months) in rats and dogs in which testicular atrophy or degeneration was observed at intravenous doses of 5 mg/kg in rats and 0.375 mg/kg in dogs (about 1/3rd and 1/15th the recommended human dose on a mg/m^2 basis, respectively). An increased frequency of dosing in rats produced similar effects at lower dose levels.

14. CLINICAL STUDIES

14.1 Locally Advanced or Metastatic Breast Cancer

The efficacy and safety of docetaxel have been evaluated in locally advanced or metastatic breast cancer after failure of previous chemotherapy (alkylating agent-containing regimens or anthracycline-containing regimens).

Randomized Trials

In one randomized trial, patients with a history of prior treatment with an anthracycline-containing regimen were assigned to treatment with docetaxel (100 mg/m^2 every 3 weeks) or the combination of mitomycin (12 mg/m^2 every 6 weeks) and vinblastine (6 mg/m^2 every 3 weeks). Two hundred three patients were randomized to docetaxel and 189 to the comparator arm. Most patients had received prior chemotherapy for metastatic disease; only 27 patients on the docetaxel arm and 33 patients on the comparator arm entered the study following relapse after adjuvant therapy. Three-quarters of patients had measurable, visceral metastases. The primary endpoint was time to progression. The following table summarizes the study results (see Table 12).

Table 12 - Efficacy of Docetaxel in the Treatment of Breast Cancer Patients Previously Treated with an Anthracycline-Containing Regimen (Intent-to-Treat Analysis)

Efficacy Parameter | Docetaxel; (n=203) | Mitomycin/ Vinblastine (n=189) | p-value
Median Survival | 11.4 months | 8.7 months | p=0.01; Log Rank
Risk Ratio [For the risk ratio, a value less than 1.00 favors docetaxel.] , Mortality (Docetaxel: Control) | 0.73 |  | p=0.01; Log Rank
95% CI (Risk Ratio) | 0.58-0.93 |  | p=0.01; Log Rank
Median Time to Progression | 4.3 months | 2.5 months
Risk Ratio, Progression (Docetaxel: Control) | 0.75 |  | p=0.01; Log Rank
95% CI (Risk Ratio) | 0.61-0.94 |  | p=0.01; Log Rank
Overall Response Rate | 28.1% | 9.5% | p<0.0001; Chi Square
Complete Response Rate | 3.4% | 1.6% | p<0.0001; Chi Square

In a second randomized trial, patients previously treated with an alkylating-containing regimen were assigned to treatment with docetaxel (100 mg/m^2) or doxorubicin (75 mg/m^2) every 3 weeks. One hundred sixty-one patients were randomized to docetaxel and 165 patients to doxorubicin. Approximately one-half of patients had received prior chemotherapy for metastatic disease, and one-half entered the study following relapse after adjuvant therapy. Three-quarters of patients had measurable, visceral metastases. The primary endpoint was time to progression. The study results are summarized below (see Table 13).

Table 13 - Efficacy of Docetaxel in the Treatment of Breast Cancer Patients Previously Treated with an Alkylating-Containing Regimen (Intent-to-Treat Analysis)

Efficacy Parameter | Docetaxel (n=161) | Doxorubicin (n=165) | p-value
Median Survival | 14.7 months | 14.3 months | p=0.39; Log Rank
Risk Ratio [For the risk ratio, a value less than 1.00 favors docetaxel.] , Mortality (Docetaxel: Control); 95% CI (Risk Ratio) | 0.89; 0.68-1.16 |  | p=0.39; Log Rank
Median Time to Progression | 6.5 months | 5.3 months | p=0.45; Log Rank
Risk Ratio, Progression (Docetaxel: Control); 95% CI (Risk Ratio) | 0.93; 0.71-1.16 |  | p=0.45; Log Rank
Overall Response Rate; Complete Response Rate | 45.3%; 6.8% | 29.7%; 4.2% | p=0.004; Chi Square

In another multicenter open-label, randomized trial (TAX313), in the treatment of patients with advanced breast cancer who progressed or relapsed after one prior chemotherapy regimen, 527 patients were randomized to receive docetaxel monotherapy 60 mg/m^2 (n=151), 75 mg/m^2 (n=188) or 100 mg/m^2 (n=188). In this trial, 94% of patients had metastatic disease and 79% had received prior anthracycline therapy. Response rate was the primary endpoint. Response rates increased with docetaxel dose: 19.9% for the 60 mg/m^2 group compared to 22.3% for the 75 mg/m^2 and 29.8% for the 100 mg/m^2 group; pair-wise comparison between the 60 mg/m^2 and 100 mg/m^2 groups was statistically significant (p=0.037).

Single Arm Studies

Docetaxel at a dose of 100 mg/m^2 was studied in six single arm studies involving a total of 309 patients with metastatic breast cancer in whom previous chemotherapy had failed. Among these, 190 patients had anthracycline-resistant breast cancer, defined as progression during an anthracycline-containing chemotherapy regimen for metastatic disease, or relapse during an anthracycline-containing adjuvant regimen. In anthracycline-resistant patients, the overall response rate was 37.9% (72/190; 95% CI: 31.0-44.8) and the complete response rate was 2.1%.

Docetaxel was also studied in three single arm Japanese studies at a dose of 60 mg/m^2, in 174 patients who had received prior chemotherapy for locally advanced or metastatic breast cancer. Among 26 patients whose best response to an anthracycline had been progression, the response rate was 34.6% (95% CI: 17.2-55.7), similar to the response rate in single arm studies of 100 mg/m^2.

14.2 Adjuvant Treatment of Breast Cancer

A multicenter, open-label, randomized trial (TAX316) evaluated the efficacy and safety of docetaxel for the adjuvant treatment of patients with axillary-node-positive breast cancer and no evidence of distant metastatic disease. After stratification according to the number of positive lymph nodes (1-3, 4+), 1491 patients were randomized to receive either docetaxel 75 mg/m^2 administered 1-hour after doxorubicin 50 mg/m^2 and cyclophosphamide 500 mg/m^2 (TAC arm), or doxorubicin 50 mg/m^2 followed by fluorouracil 500 mg/m^2 and cyclophosphamide 500 mg/m^2 (FAC arm). Both regimens were administered every 3 weeks for 6 cycles. Docetaxel was administered as a 1-hour infusion; all other drugs were given as intravenous bolus on day 1. In both arms, after the last cycle of chemotherapy, patients with positive estrogen and/or progesterone receptors received tamoxifen 20 mg daily for up to 5 years. Adjuvant radiation therapy was prescribed according to guidelines in place at participating institutions and was given to 69% of patients who received TAC and 72% of patients who received FAC.

Results from a second interim analysis (median follow-up 55 months) are as follows: In study TAX316, the docetaxel-containing combination regimen TAC showed significantly longer disease-free survival (DFS) than FAC (hazard ratio=0.74; 2-sided 95% CI=0.60, 0.92, stratified log rank p=0.0047). The primary endpoint, disease-free survival, included local and distant recurrences, contralateral breast cancer and deaths from any cause. The overall reduction in risk of relapse was 25.7% for TAC-treated patients (see Figure 1).

At the time of this interim analysis, based on 219 deaths, overall survival was longer for TAC than FAC (hazard ratio=0.69, 2-sided 95% CI=0.53, 0.90) (see Figure 2). There will be further analysis at the time survival data mature.

Figure 1 - TAX316 Disease Free Survival K-M Curve

Figure 2 - TAX316 Overall Survival K-M Curve

The following table describes the results of subgroup analyses for DFS and OS (see Table 14).

Table 14 - Subset Analyses-Adjuvant Breast Cancer Study

 |  | Disease Free Survival |  | Overall Survival
Patient subset | Number of patients | Hazard ratio [A hazard ratio of less than 1 indicates that TAC is associated with a longer disease-free survival or overall survival compared to FAC.] | 95% CI | Hazard ratio | 95% CI
No. of positive nodes
Overall | 744 | 0.74 | (0.60, 0.92) | 0.69 | (0.53, 0.90)
1-3 | 467 | 0.64 | (0.47, 0.87) | 0.45 | (0.29, 0.70)
4+ | 277 | 0.84 | (0.63, 1.12) | 0.93 | (0.66, 1.32)
Receptor status
Positive | 566 | 0.76 | (0.59, 0.98) | 0.69 | (0.48, 0.99)
Negative | 178 | 0.68 | (0.48, 0.97) | 0.66 | (0.44, 0.98)

14.3 Non-Small Cell Lung Cancer (NSCLC)

The efficacy and safety of docetaxel has been evaluated in patients with unresectable, locally advanced or metastatic non-small cell lung cancer whose disease has failed prior platinum-based chemotherapy or in patients who are chemotherapy-naive.

Monotherapy with Docetaxel for NSCLC Previously Treated with Platinum-Based Chemotherapy

Two randomized, controlled trials established that a docetaxel dose of 75 mg/m^2 was tolerable and yielded a favorable outcome in patients previously treated with platinum-based chemotherapy (see below). Docetaxel at a dose of 100 mg/m^2, however, was associated with unacceptable hematologic toxicity, infections, and treatment-related mortality and this dose should not be used [see Boxed Warning, Dosage and Administration (2.7), Warnings and Precautions (5.3)].

One trial (TAX317), randomized patients with locally advanced or metastatic non-small cell lung cancer, a history of prior platinum-based chemotherapy, no history of taxane exposure, and an ECOG performance status ≤2 to docetaxel or best supportive care. The primary endpoint of the study was survival. Patients were initially randomized to docetaxel 100 mg/m^2 or best supportive care, but early toxic deaths at this dose led to a dose reduction to docetaxel 75 mg/m^2. A total of 104 patients were randomized in this amended study to either docetaxel 75 mg/m^2 or best supportive care.

In a second randomized trial (TAX320), 373 patients with locally advanced or metastatic non-small cell lung cancer, a history of prior platinum-based chemotherapy, and an ECOG performance status ≤2 were randomized to docetaxel 75 mg/m^2, docetaxel 100 mg/m^2 and a treatment in which the investigator chose either vinorelbine 30 mg/m^2 days 1, 8, and 15 repeated every 3 weeks or ifosfamide 2 g/m^2 days 1-3 repeated every 3 weeks. Forty percent of the patients in this study had a history of prior paclitaxel exposure. The primary endpoint was survival in both trials. The efficacy data for the docetaxel 75 mg/m^2 arm and the comparator arms are summarized in Table 15 and Figures 3 and 4 showing the survival curves for the two studies.

Table 15 - Efficacy of Docetaxel in the Treatment of Non-Small Cell Lung Cancer Patients Previously Treated with a Platinum-Based Chemotherapy Regimen (Intent-to-Treat Analysis)

 | TAX317 |  | TAX320
 | Docetaxel | Best | Docetaxel | Control
 | 75 mg/m^2 n=55 | Supportive Care; n=49 | 75 mg/m^2 n=125 | (V/I [Vinorelbine/Ifosfamide]) n=123
Overall Survival; Log-rank Test | p=0.01 |  | p=0.13
Risk Ratio [a value less than 1.00 favors docetaxel.] , Mortality (Docetaxel: Control) | 0.56 |  | 0.82
95% CI (Risk Ratio) | (0.35, 0.88) |  | (0.63, 1.06)
Median Survival | 7.5 months | 4.6 months | 5.7 months | 5.6 months
95% CI | (5.5, 12.8) | (3.7, 6.1) | (5.1, 7.1) | (4.4, 7.9)
% 1-year Survival | 37% [p≤0.05] [uncorrected for multiple comparisons.] | 12% | 30% | 20%
95% CI | (24, 50) | (2, 23) | (22, 39) | (13, 27)
Time to Progression | 12.3 weeks | 7.0 weeks | 8.3 weeks | 7.6 weeks
95% CI | (9.0, 18.3) | (6.0, 9.3) | (7.0,11.7) | (6.7, 10.1)
Response Rate | 5.5% | Not Applicable | 5.7% | 0.8%
95% CI | (1.1, 15.1) | Not Applicable | (2.3,11.3) | (0.0, 4.5)

Only one of the two trials (TAX317) showed a clear effect on survival, the primary endpoint; that trial also showed an increased rate of survival to one year. In the second study (TAX320) the rate of survival at one year favored docetaxel 75 mg/m^2.

Figure 3 - TAX317 Survival K-M Curves - Docetaxel 75 mg/m^2 versus Best Supportive Care

Figure 4 - TAX320 Survival K-M Curves - Docetaxel 75 mg/m^2 versus Vinorelbine or Ifosfamide Control

Patients treated with docetaxel at a dose of 75 mg/m^2 experienced no deterioration in performance status and body weight relative to the comparator arms used in these trials.

Combination Therapy with Docetaxel for Chemotherapy-Naive NSCLC

In a randomized controlled trial (TAX326), 1218 patients with unresectable stage IIIB or IV NSCLC and no prior chemotherapy were randomized to receive one of three treatments: docetaxel 75 mg/m^2 as a 1 -hour infusion immediately followed by cisplatin 75 mg/m^2 over 30 to 60 minutes every 3 weeks; vinorelbine 25 mg/m^2 administered over 6 to 10 minutes on days 1, 8, 15, 22 followed by cisplatin 100 mg/m^2 administered on day 1 of cycles repeated every 4 -weeks; or a combination of docetaxel and carboplatin.

The primary efficacy endpoint was overall survival. Treatment with docetaxel+cisplatin did not result in a statistically significantly superior survival compared to vinorelbine+cisplatin (see table below). The 95% confidence interval of the hazard ratio (adjusted for interim analysis and multiple comparisons) shows that the addition of docetaxel to cisplatin results in an outcome ranging from a 6% inferior to a 26% superior survival compared to the addition of vinorelbine to cisplatin. The results of a further statistical analysis showed that at least (the lower bound of the 95% confidence interval) 62% of the known survival effect of vinorelbine when added to cisplatin (about a 2-month increase in median survival; Wozniak et al. JCO, 1998) was maintained. The efficacy data for the docetaxel+cisplatin arm and the comparator arm are summarized in Table 16.

Table 16 - Survival Analysis of Docetaxel in Combination Therapy for Chemotherapy-Naive NSCLC

Comparison | Docetaxel+Cisplatin n=408 | Vinorelbine+Cisplatin; n=405
Kaplan-Meier Estimate of Median Survival | 10.9 months | 10 months
p-value [From the superiority test (stratified log rank) comparing docetaxel+cisplatin to vinorelbine+cisplatin] | 0.122
Estimated Hazard Ratio [Hazard ratio of docetaxel+cisplatin versus vinorelbine+cisplatin. A hazard ratio of less than 1 indicates that docetaxel+cisplatin is associated with a longer survival.] | 0.88
Adjusted 95% CI [Adjusted for interim analysis and multiple comparisons.] | (0.74, 1.06)

The second comparison in the same three-arm study, vinorelbine+cisplatin versus docetaxel+carboplatin, did not demonstrate superior survival associated with the docetaxel arm (Kaplan-Meier estimate of median survival was 9.1 months for docetaxel+carboplatin compared to 10.0 months on the vinorelbine+cisplatin arm) and the docetaxel+carboplatin arm did not demonstrate preservation of at least 50% of the survival effect of vinorelbine added to cisplatin. Secondary endpoints evaluated in the trial included objective response and time to progression. There was no statistically significant difference between docetaxel+cisplatin and vinorelbine+cisplatin with respect to objective response and time to progression (see Table 17).

Table 17 - Response and TTP Analysis of Docetaxel in Combination Therapy for Chemotherapy-Naive NSCLC

Endpoint | Docetaxel +Cisplatin | Vinorelbine+Cisplatin | p-value
Objective Response Rate; (95% CI) [Adjusted for multiple comparisons.] | 31.6%; (26.5%, 36.8%) | 24.4%; (19.8%, 29.2%) | Not Significant
Median Time to Progression [Kaplan-Meier estimates.]; (95% CI) | 21.4 weeks; (19.3, 24.6) | 22.1 weeks; (18.1, 25.6) | Not Significant

14.4 Castration-Resistant Prostate Cancer

The safety and efficacy of docetaxel in combination with prednisone in patients with metastatic castration-resistant prostate cancer were evaluated in a randomized multicenter active control trial. A total of 1006 patients with Karnofsky Performance Status (KPS) ≥60 were randomized to the following treatment groups:

- Docetaxel 75 mg/m^2 every 3 weeks for 10 cycles.
- Docetaxel 30 mg/m^2 administered weekly for the first 5 weeks in a 6-week cycle for 5 cycles.
- Mitoxantrone 12 mg/m^2 every 3 weeks for 10 cycles.

All 3 regimens were administered in combination with prednisone 5 mg twice daily, continuously.

In the docetaxel every three-week arm, a statistically significant overall survival advantage was demonstrated compared to mitoxantrone. In the docetaxel weekly arm, no overall survival advantage was demonstrated compared to the mitoxantrone control arm. Efficacy results for the docetaxel every 3-week arm versus the control arm are summarized in Table 18 and Figure 5.

Table 18 - Efficacy of Docetaxel in the Treatment of Patients with Metastatic Castration-Resistant Prostate Cancer (Intent-to-Treat Analysis)

 | Docetaxel + Prednisone | Mitoxantrone+ Prednisone
 | every 3 weeks | every 3 weeks
Number of patients | 335 | 337
Median survival (months) | 18.9 | 16.5
95% CI | (17.0-21.2) | (14.4-18.6)
Hazard ratio | 0.761 | -
95% CI | (0.619-0.936) | -
p-value [Stratified log -rank test. Threshold for statistical significance = 0.0175 because of 3 arms.] | 0.0094 | -

Figure 5 - TAX327 Survival K-M Curves

14.5 Gastric Adenocarcinoma

A multicenter, open-label, randomized trial was conducted to evaluate the safety and efficacy of docetaxel injection for the treatment of patients with advanced gastric adenocarcinoma, including adenocarcinoma of the gastroesophageal junction, who had not received prior chemotherapy for advanced disease. A total of 445 patients with KPS >70 were treated with either docetaxel injection (T) (75 mg/m^2 on day 1) in combination with cisplatin (C) (75 mg/m^2 on day 1) and fluorouracil (F) (750 mg/m^2 per day for 5 days) or cisplatin (100 mg/m^2 on day 1) and fluorouracil (1000 mg/m^2 per day for 5 days). The length of a treatment cycle was 3 weeks for the TCF arm and 4 weeks for the CF arm. The demographic characteristics were balanced between the two treatment arms. The median age was 55 years, 71% were male, 71% were Caucasian, 24% were 65 years of age or older, 19% had a prior curative surgery and 12% had palliative surgery. The median number of cycles administered per patient was 6 (with a range of 1 to 16) for the TCF arm compared to 4 (with a range of 1 to 12) for the CF arm. Time to progression (TTP) was the primary endpoint and was defined as time from randomization to disease progression or death from any cause within 12 weeks of the last evaluable tumor assessment or within 12 weeks of the first infusion of study drugs for patients with no evaluable tumor assessment after randomization. The hazard ratio (HR) for TTP was 1.47 (CF/TCF, 95% CI: 1.19 to 1.83) with a significantly longer TTP (p=0.0004) in the TCF arm. Approximately 75% of patients had died at the time of this analysis. Overall survival was significantly longer (p=0.0201) in the TCF arm with a HR of 1.29 (95% CI: 1.04 to 1.61). Efficacy results are summarized in Table 19 and Figures 6 and 7.

Table 19 - Efficacy of Docetaxel Injection in the Treatment of Patients with Gastric Adenocarcinoma

Endpoint | TCF; n=221 | CF; n=224
Median TTP (months); (95% CI); Hazard ratio [For the hazard ratio (TCF/CF), values less than 1.00 favor the docetaxel injection arm.]; (95% CI); [Unstratified log-rank test.] p-value | 5.6; (4.86-5.91) | 3.7; (3.45-4.47)
Median TTP (months); (95% CI); Hazard ratio [For the hazard ratio (TCF/CF), values less than 1.00 favor the docetaxel injection arm.]; (95% CI); [Unstratified log-rank test.] p-value | 0.68; (0.55-0.84); 0.0004
Median survival (months); (95% CI); Hazard ratio; (95% CI); p-value | 9.2; (8.38-10.58) | 8.6; (7.16-9.46)
Median survival (months); (95% CI); Hazard ratio; (95% CI); p-value | 0.77; (0.62-0.96); 0.0201
Overall Response Rate (CR+PR) (%); p-value | 36.7 | 25.4
Overall Response Rate (CR+PR) (%); p-value | 0.0106

Subgroup analyses were consistent with the overall results across age, gender and race.

Figure 6 - Gastric Cancer Study (TAX325) Time to Progression K-M Curve

Figure 7 - Gastric Cancer Study (TAX325) Survival K-M Curve

14.6 Head and Neck Cancer

Induction Chemotherapy Followed by Radiotherapy (TAX323)

The safety and efficacy of docetaxel injection in the induction treatment of patients with squamous cell carcinoma of the head and neck (SCCHN) was evaluated in a multicenter, open-label, randomized trial (TAX323). In this study, 358 patients with inoperable locally advanced SCCHN, and WHO performance status 0 or 1, were randomized to one of two treatment arms. Patients on the docetaxel injection arm received docetaxel injection (T) 75 mg/m^2 followed by cisplatin (P) 75 mg/m^2 on Day 1, followed by fluorouracil (F) 750 mg/m^2 per day as a continuous infusion on Days 1 to 5. The cycles were repeated every three weeks for 4 cycles. Patients whose disease did not progress received radiotherapy (RT) according to institutional guidelines (TPF/RT). Patients on the comparator arm received cisplatin (P) 100 mg/m^2 on Day 1, followed by fluorouracil (F) 1000 mg/m^2 /day as a continuous infusion on Days 1 to 5. The cycles were repeated every three weeks for 4 cycles. Patients whose disease did not progress received RT according to institutional guidelines (PF/RT). At the end of chemotherapy, with a minimal interval of 4 weeks and a maximal interval of 7 weeks, patients whose disease did not progress received radiotherapy (RT) according to institutional guidelines. Locoregional therapy with radiation was delivered either with a conventional fraction regimen (1.8 Gy to 2 Gy once a day, 5 days per week for a total dose of 66 to 70 Gy) or with an accelerated/hyperfractionated regimen (twice a day, with a minimum interfraction interval of 6 hours, 5 days per week, for a total dose of 70 to 74 Gy, respectively). Surgical resection was allowed following chemotherapy, before or after radiotherapy.

The primary endpoint in this study, progression-free survival (PFS), was significantly longer in the TPF arm compared to the PF arm, p=0.0077 (median PFS: 11.4 vs. 8.3 months respectively) with an overall median follow up time of 33.7 months. Median overall survival with a median follow-up of 51.2 months was also significantly longer in favor of the TPF arm compared to the PF arm (median OS: 18.6 vs. 14.2 months respectively). Efficacy results are presented in Table 20 and Figures 8 and 9.

Table 20 - Efficacy of Docetaxel Injection in the Induction Treatment of Patients with Inoperable Locally Advanced SCCHN (Intent-to-Treat Analysis)

Endpoint | Docetaxel Injection + Cisplatin+ Fluorouracil; n=177 | Cisplatin+ Fluorouracil; n=181
Median progression free survival (months) | 11.4 | 8.3
(95% CI) | (10.1-14.0) | (7.4-9.1)
Adjusted Hazard ratio; (95% CI); [Stratified log-rank test based on primary tumor site.] p-value | 0.71; (0.56-0.91); 0.0077
Median survival (months) (95% CI) | 18.6; (15.7-24.0) | 14.2; (11.5-18.7)
Hazard ratio; (95% CI); [Stratified log-rank test, not adjusted for multiple comparisons.] p-value | 0.71; (0.56-0.90); 0.0055
Best overall response (CR + PR) to chemotherapy (%); (95% CI) | 67.8; (60.4-74.6) | 53.6; (46.0-61.0)
[Chi square test, not adjusted for multiple comparisons.] p-value | 0.006
Best overall response (CR + PR) to study treatment [chemotherapy +/- radiotherapy] (%) | 72.3 | 58.6
(95% CI) | (65.1-78.8) | (51.0-65.8)
p-value | 0.006
A Hazard ratio of less than 1 favors docetaxel injection+cisplatin+fluorouracil

Figure 8 - TAX323 Progression-Free Survival K-M Curve

Figure 9 - TAX323 Overall Survival K-M Curve

Induction Chemotherapy Followed by Chemoradiotherapy (TAX324)

The safety and efficacy of docetaxel injection in the induction treatment of patients with locally advanced (unresectable, low surgical cure, or organ preservation) SCCHN was evaluated in a randomized, multicenter open-label trial (TAX324). In this study, 501 patients, with locally advanced SCCHN, and a WHO performance status of 0 or 1, were randomized to one of two treatment arms. Patients on the docetaxel injection arm received docetaxel injection (T) 75 mg/m^2 by intravenous infusion on day 1 followed by cisplatin (P) 100 mg/m^2 administered as a 30-minute to three-hour intravenous infusion, followed by the continuous intravenous infusion of fluorouracil (F) 1000 mg/m^2/day from day 1 to day 4. The cycles were repeated every 3 weeks for 3 cycles. Patients on the comparator arm received cisplatin (P) 100 mg/m^2 as a 30-minute to three-hour intravenous infusion on day 1 followed by the continuous intravenous infusion of fluorouracil (F) 1000 mg/m^2/day from day 1 to day 5. The cycles were repeated every 3 weeks for 3 cycles.

All patients in both treatment arms who did not have progressive disease were to receive 7 weeks of chemoradiotherapy (CRT) following induction chemotherapy 3 to 8 weeks after the start of the last cycle. During radiotherapy, carboplatin (AUC 1.5) was given weekly as a one-hour intravenous infusion for a maximum of 7 doses. Radiation was delivered with megavoltage equipment using once daily fractionation (2 Gy per day, 5 days per week for 7 weeks for a total dose of 70-72 Gy). Surgery on the primary site of disease and/or neck could be considered at any time following completion of CRT.

The primary efficacy endpoint, overall survival (OS), was significantly longer (log-rank test, p=0.0058) with the docetaxel injection-containing regimen compared to PF (median OS: 70.6 vs 30.1 months, respectively, hazard ratio [HR]=0.70, 95% confidence interval [CI]= 0.54 to 0.90). Overall survival results are presented in Table 21 and Figure 10.

Table 21 - Efficacy of Docetaxel Injection in the Induction Treatment of Patients with Locally Advanced SCCHN (Intent-to-Treat Analysis)

Endpoint | Docetaxel Injection + Cisplatin+ Fluorouracil; n=255 | Cisplatin+ Fluorouracil; n=246
Median overall survival (months) (95% CI) | 70.6; (49.0-NE) | 30.1; (20.9-51.5)
Hazard ratio:; (95% CI); [un-adjusted log-rank test] p-value | 0.70; (0.54-0.90); 0.0058
A Hazard ratio of less than 1 favors docetaxel injection+cisplatin+fluorouracil.
NE - not estimable.

Figure 10 - TAX324 Overall Survival K-M Curve

15. REFERENCES

1. “OSHA Hazardous Drugs.” http://www.osha.gov/SLTC/hazardousdrugs/index.html

16. HOW SUPPLIED/STORAGE AND HANDLING

16.1 How Supplied

Docetaxel Injection is supplied in a multiple-dose vial as a sterile, pyrogen-free solution. Docetaxel Injection requires NO prior dilution with a diluent and is ready to add to the infusion solution. The following strengths are available:

Strength | NDC Number | Volume
20 mg/2 mL | 43066-001-01 | Carton of one 2 mL Multiple-Dose Vial
80 mg/8 mL | 43066-006-01 | Carton of one 8 mL Multiple-Dose Vial
160 mg/16 mL | 43066-010-01 | Carton of one 16 mL Multiple-Dose Vial

16.2 Storage

Store between 2°C and 25°C (36°F and 77°F). Retain in the original package to protect from bright light. Freezing does not adversely affect the product.

After initial puncture, Docetaxel Injection multiple-dose vials are stable for 28 days when stored between 2ºC to 8ºC and at room temperature, with or without protection from light.

16.3 Handling and Disposal

Docetaxel Injection is a hazardous drug. Follow applicable special handling and disposal procedures.^1

17. PATIENT COUNSELING INFORMATION

Advise the patient to read the FDA-approved patient labeling (Patient Information).

Bone Marrow Suppression

Advise patients that periodic assessment of their blood count will be performed to detect neutropenia, thrombocytopenia, and/ or anemia [see Contraindications (4), Warnings and Precautions (5.3)]. Instruct patients to monitor their temperature frequently and immediately report any occurrence of fever.

Enterocolitis and Neutropenic Colitis

Advise patients of the symptoms of colitis, such as abdominal pain or tenderness, and/or diarrhea, with or without fever, and instruct patients to promptly contact their healthcare provider if they experience these symptoms [see Dosage and Administration (2.7) and Warnings and Precautions (5.4)].

Hypersensitivity Reactions

Ask patients whether they have previously received paclitaxel therapy, and if they have experienced a hypersensitivity reaction to paclitaxel. Instruct patients to immediately report to their healthcare provider signs of a hypersensitivity reaction [see Contraindications (4), Warnings and Precautions (5.5)].

Fluid Retention

Advise patients to report signs of fluid retention such as peripheral edema in the lower extremities, weight gain, and dyspnea immediately to their healthcare provider [see Warnings and Precautions (5.6)].

Second Primary Malignancies

Advise patients on the risk of second primary malignancies during treatment with docetaxel [see Warnings and Precautions (5.7)].

Cutaneous Reactions

Advise patients that localized erythema of the extremities and severe skin toxicities may occur. Instruct patients to immediately report severe cutaneous reactions to their healthcare provider [see Dosage and Administration (2.7) and Warnings and Precautions (5.8)].

Neurologic Reactions

Advise patients that neurosensory symptoms or peripheral neuropathy may occur. Instruct patients to immediately report neurologic reactions to their healthcare provider [see Dosage and Administration (2.7) and Warnings and Precautions (5.9)].

Eye Disorders

Advise patients that vision disturbances and excessive tearing are associated with Docetaxel Injection administration. Instruct patients to immediately report any vision changes to their healthcare provider [see Warnings and Precautions (5.10)].

Gastrointestinal Reactions

Explain to patients that nausea, vomiting, diarrhea, and constipation are associated with Docetaxel Injection administration. Instruct patients to report any severe events to their healthcare provider [see Adverse Reactions (6)].

Cardiac Disorders

Advise patients to report any irregular and/or rapid heartbeat, severe shortness of breath, dizziness, and/or fainting immediately to their healthcare provider [see Adverse Reactions (6)].

Other Common Adverse Reactions

Advise patients that other common adverse reactions associated with Docetaxel Injection may include alopecia (cases of permanent hair loss have been reported), asthenia, anorexia, dysgeusia, mucositis, myalgia, nail disorders, or pain. Instruct patients to report these reactions to their healthcare provider if serious events occur [see Adverse Reactions (6)].

Importance of Corticosteroids

Explain the significance of oral corticosteroids such as dexamethasone administration to the patient to help facilitate compliance. Instruct patients to report to their healthcare provider if they were not compliant with the oral corticosteroid regimen [see Dosage and Administration (2.6)].

Embryo-Fetal Toxicity

Docetaxel Injection can cause fetal harm. Advise patients to inform their healthcare provider of a known or suspected pregnancy. Advise patients to avoid becoming pregnant while receiving this drug. Advise female patients of reproductive potential to use effective contraceptives during treatment and for 2 months after the last dose of Docetaxel Injection. Advise male patients with female partners of reproductive potential to use effective contraception during treatment and for 4 months after the last dose of Docetaxel Injection [see Warnings and Precautions (5.12), and Use in Specific Populations (8.1, 8.3)].

Lactation

Advise women not to breastfeed during Docetaxel Injection treatment and for 1 week after the last dose [see Use in Specific Populations (8.2)].

Infertility

Advise males of reproductive potential that Docetaxel Injection may impair fertility [see Nonclinical Toxicology (13.1)].

Alcohol Content in Docetaxel Injection

Explain to patients the possible effects of the alcohol content in Docetaxel Injection, including possible effects on the central nervous system [see Warnings and Precautions (5.13)].

Tumor Lysis Syndrome

Advise patients of the potential risk of tumor lysis syndrome and to immediately report any signs or symptoms associated with this event (nausea, vomiting, confusion, shortness of breath, seizure, irregular heartbeat, dark or cloudy urine, reduced amount of urine, unusual tiredness, muscle cramps) to their healthcare provider. Advise patients of the importance of keeping scheduled appointment for blood work or other laboratory tests and of drinking adequate fluids to avoid dehydration [see Warnings and Precautions (5.14)].

Ability to Drive or Operate Machines

Explain to patients that Docetaxel Injection may impair their ability to drive or operate machines due to its side effects [see Adverse Reactions (6)] or due to the alcohol content of Docetaxel Injection [see Warnings and Precautions (5.13)]. Advise them not to drive or use machines if they experience these side effects during treatment.

Drug Interactions

Inform patients about the risk of drug interactions and the importance of providing a list of prescription and non-prescription drugs to their healthcare provider [see Drug Interactions (7)].

Manufactured by FAREVA Unterach GmbH for

Sandoz Inc., Princeton, NJ 08540

Baxter is a registered trademark of Baxter International Inc.

Patient Information

Docetaxel (doe-se-TAKS-el) Injection

for intravenous use

What is the most important information I should know about Docetaxel Injection?

Docetaxel Injection can cause serious side effects, including death.

- The chance of death in people who receive Docetaxel Injection is higher if you:
- have liver problems
- receive high doses of Docetaxel Injection
- have non-small cell lung cancer and have been treated with chemotherapy medicines that contain platinum
- Docetaxel Injection can affect your blood cells. Your healthcare provider should do routine blood tests during treatment with Docetaxel Injection. This will include regular checks of your white blood cell counts. If your white blood cells are too low, your healthcare provider may not treat you with Docetaxel Injection until you have enough white blood cells. People with low white blood cell counts can develop life-threatening infections. The earliest sign of infection may be fever. Follow your healthcare provider's instructions for how often to take your temperature during treatment with Docetaxel Injection. Call your healthcare provider right away if you have a fever.
- Swelling (inflammation) of the small intestine and colon. This can happen at any time during treatment and could lead to death as early as the first day you get symptoms. Tell your healthcare provider right away if you develop new or worse symptoms of intestinal problems, including stomach (abdominal) pain or tenderness or diarrhea, with or without fever.
- Severe allergic reactions are medical emergencies that can happen in people who receive Docetaxel Injection and can lead to death. You may be at higher risk of developing a severe allergic reaction to Docetaxel Injection if you are allergic to paclitaxel. Your healthcare provider will monitor you closely for allergic reactions during your Docetaxel Injection infusion.
Tell your healthcare provider right away if you have any of these signs of a severe allergic reaction:
- trouble breathing
- sudden swelling of your face, lips, tongue, throat, or trouble swallowing
- hives (raised bumps), rash, or redness all over your body
- Your body may hold too much fluid (severe fluid retention) during treatment with Docetaxel Injection. This can be life threatening. To decrease the chance of this happening, you must take another medicine, a corticosteroid, before each Docetaxel Injection treatment. You must take the corticosteroid exactly as your healthcare provider tells you. Tell your healthcare provider or nurse before your Docetaxel Injection treatment if you forgot to take your corticosteroid dose or do not take it as your healthcare provider tells you. Tell your healthcare provider right away if you have swelling in your legs or feet, weight gain, or shortness of breath.
- Risk of new cancers. An increase in new (second) cancers has happened in people treated with Docetaxel Injection together with certain other anticancer treatments. This includes certain blood cancers, such as acute myeloid leukemia (AML), myelodysplastic syndrome (MDS), non-Hodgkin’s Lymphoma (NHL), and kidney cancer.
- Changes in blood counts due to leukemia and other blood disorders may occur years after treatment with Docetaxel Injection.
Your healthcare provider will check you for new cancers during and after your treatment with Docetaxel Injection.
- Severe skin problems.
Tell your healthcare provider right away if you have any of these signs of a severe skin reaction:
- redness and swelling of your arms and legs.
- blistering, peeling or bleeding on any part of your skin (including your lips, eyes, mouth, nose, genitals, hands or feet) with or without a rash. You may also have flu-like symptoms such as fever, chills, or muscle aches.
- red, scaly rash all over your body with blisters small red or white bumps under the skin that contain pus (pustules) and fever.

What is Docetaxel Injection?

Docetaxel Injection is a prescription anticancer medicine used to treat certain people with:

- breast cancer
- non-small cell lung cancer
- prostate cancer
- stomach cancer
- head and neck cancer

It is not known if Docetaxel Injection is effective in children.

Do not receive Docetaxel Injection if you:

- have a low white blood cell count
- have had a severe allergic reaction to:
  - docetaxel, the active ingredient in Docetaxel Injection, or
  - any other medicines that contain polysorbate 80. Ask your healthcare provider or pharmacist if you are not sure.
See "What is the most important information I should know about Docetaxel Injection?" for the signs and symptoms of a severe allergic reaction.

See the end of this Patient Information for a complete list of the ingredients in Docetaxel Injection.

Before you receive Docetaxel Injection, tell your healthcare provider about all of your medical conditions, including if you:

- are allergic to any medicines, including paclitaxel. See "Do not receive Docetaxel Injection if you".
- have liver problems
- have kidney problems
- are pregnant or plan to become pregnant. Docetaxel Injection can harm your unborn baby. You should not become pregnant during treatment with Docetaxel Injection. Tell your healthcare provider if you become pregnant or you think you may be pregnant during treatment with Docetaxel Injection.
Females who are able to become pregnant:
- Your healthcare provider will check to see if you are pregnant before you start treatment with Docetaxel Injection.
- You should use effective birth control (contraception) during treatment with Docetaxel Injection and for 6 months after the last dose.
Males with female partners who are able to become pregnant should use effective birth control during treatment with Docetaxel Injection and for 3 months after the last dose.
Talk to your healthcare provider if you have questions about birth control options that are right for you.
- are breastfeeding or plan to breastfeed. It is not known if Docetaxel Injection passes into your breast milk. Do not breastfeed during treatment with Docetaxel Injection and for 1 week after the last dose.

Tell your healthcare provider about all the medicines you take, including prescription and over-the-counter medicines, vitamins, and herbal supplements. Docetaxel Injection may affect the way other medicines work, and other medicines may affect the way Docetaxel Injection works. Know the medicines you take. Keep a list of them to show your healthcare provider and pharmacist when you get a new medicine.

How will I receive Docetaxel Injection?

- Docetaxel Injection will be given to you as an intravenous (IV) injection into your vein, usually over 1 hour.
- Docetaxel Injection is usually given every 3 weeks.
- Your healthcare provider will decide how long you will receive treatment with Docetaxel Injection.
- Your healthcare provider will check your blood cell counts and other blood tests during your treatment with Docetaxel Injection to check for side effects of Docetaxel Injection.
- Your healthcare provider may stop your treatment, change the timing of your treatment, or change the dose of your treatment if you have certain side effects while receiving Docetaxel Injection.

What are the possible side effects of Docetaxel Injection?

Docetaxel Injection may cause serious side effects including death.

- See "What is the most important information I should know about Docetaxel Injection?"
- Neurologic problems. Neurologic symptoms are common in people who receive Docetaxel Injection but can be severe. Tell your healthcare provider right away if you have numbness, tingling, or burning in your hands or feet (peripheral neuropathy) or weakness of your legs, feet, arms, or hands (motor weakness).
- Vision problems including blurred vision or loss of vision. Tell your healthcare provider right away if you have any vision changes.
- Docetaxel Injection contains alcohol. The alcohol content in Docetaxel Injection may impair your ability to drive or use machinery right after receiving Docetaxel Injection. Consider whether you should drive, operate machinery or do other dangerous activities right after you receive Docetaxel Injection treatment.
- Tumor lysis syndrome (TLS). TLS is caused by the fast breakdown of cancer cells. TLS can cause kidney failure, the need for dialysis treatment, or heart problems, and may lead to death. Your healthcare provider will do blood tests to check for TLS when you first start treatment and during treatment with Docetaxel Injection. Tell your healthcare provider right away if you have any symptoms of TLS during treatment with Docetaxel Injection, including:
  - nausea
  - vomiting
  - confusion
  - shortness of breath
  - irregular heartbeat
  - dark or cloudy urine
  - reduced amount of urine
  - unusual tiredness
  - muscle cramps
- You may experience side effects of Docetaxel Injection that may impair your ability to drive, use tools, or operate machines. If this happens, do not drive or use any tools or machines before discussing with your healthcare provider.

The most common side effects of Docetaxel Injection include:

- infections
- low white blood cells (help fight infections), low red blood cells (anemia), and low platelets (help blood to clot)
- allergic reactions (See “What is the most important information I should know about Docetaxel Injection?”)
- changes in your sense of taste
- shortness of breath
- constipation
- decreased appetite
- changes in your fingernails or toenails
- swelling of your hands, face or feet
- feeling weak or tired
- joint and muscle pain
- nausea and vomiting
- diarrhea
- mouth or lips sores
- hair loss: in some people, permanent hair loss has been reported
- redness of the eye, excess tearing
- skin reactions at the site of Docetaxel Injection administration such as increased skin pigmentation, redness, tenderness, swelling, warmth or dryness of the skin
- tissue damage if Docetaxel Injection leaks out of the vein into the tissues

Tell your healthcare provider if you have a fast or irregular heartbeat, severe shortness of breath, dizziness or fainting during your infusion. If any of these events occurs after your infusion, get medical help right away.

Docetaxel Injection may affect fertility in males. Talk to your healthcare provider if this is a concern for you.

These are not all the possible side effects of Docetaxel Injection. For more information ask your healthcare provider or pharmacist.

Call your healthcare provider for medical advice about side effects. You may report side effects to FDA at 1-800-FDA-1088.

General information about the safe and effective use of Docetaxel Injection.

Medicines are sometimes prescribed for purposes other than those listed in this Patient Information. You can ask your pharmacist or healthcare provider for information about Docetaxel Injection that is written for health professionals.

What are the ingredients in Docetaxel Injection?

Active ingredient: docetaxel

Inactive ingredients: alcohol, citric acid, polyethylene glycol 300, and polysorbate 80

Manufactured by FAREVA Unterach GmbH for

Sandoz Inc., Princeton, NJ 08540

Baxter is a registered trademark of Baxter International Inc.

For more information, call 1-800-525-8747.

This Patient Information has been approved by the U.S. Food and Drug Administration. Revised: November 2023

Every three-week injection of Docetaxel Injection for breast, non-small cell lung and stomach, and head and neck cancers

Take your oral corticosteroid medicine as your healthcare provider tells you.

Oral corticosteroid dosing:

Day 1 Date:________ Time: ________ AM_____ PM

Day 2 Date:________ Time: ________ AM_____ PM

(Docetaxel Injection Treatment Day)

Day 3 Date:________ Time: ________ AM_____ PM ________

Every three-week injection of Docetaxel Injection for prostate cancer

Take your oral corticosteroid medicine as your healthcare provider tells you.

Oral corticosteroid dosing:

Date:________ Time: ________

Date:________ Time: ________

(Docetaxel Injection Treatment Day)

Time: ________

Package/Label Principal Display Panel

NDC 43066-001-01

2 mL Multiple-Dose Vial

Docetaxel

Injection

20 mg/2mL

(10 mg/mL)

For Intravenous Infusion Only

Caution: Cytotoxic Agent

Rx Only

Ready to add to infusion solution.

Check concentration prior to preparation.

See package insert for complete instructions.

Baxter

Package/Label Principal Display Panel

NDC 43066-006-01

8 mL Multiple-Dose Vial

Docetaxel

Injection

80 mg/8mL

(10 mg/mL)

For Intravenous Infusion Only

Caution: Cytotoxic Agent

Rx Only

Ready to add to infusion solution.

Check concentration prior to preparation.

See package insert for complete instructions.

Baxter

Package/Label Principal Display Panel

NDC 43066-010-01

16 mL Multiple-Dose Vial

Docetaxel

Injection

160 mg/16mL

(10 mg/mL)

For Intravenous Infusion Only

Caution: Cytotoxic Agent

Rx Only

Ready to add to infusion solution.

Check concentration prior to preparation.

See package insert for complete instructions.

Baxter